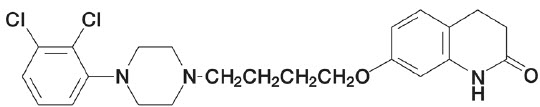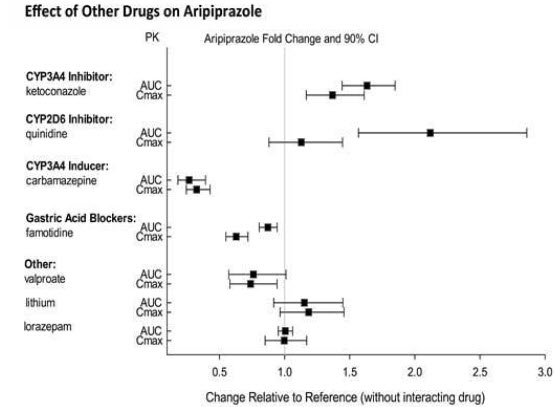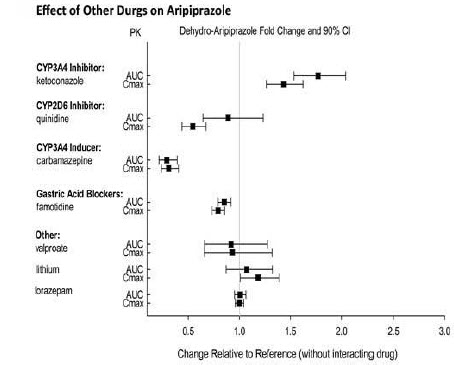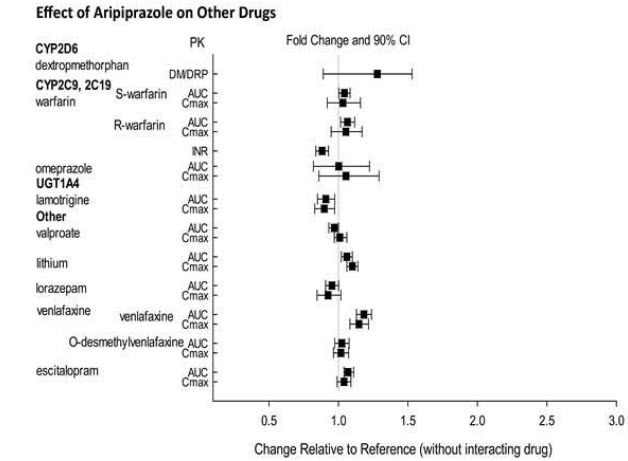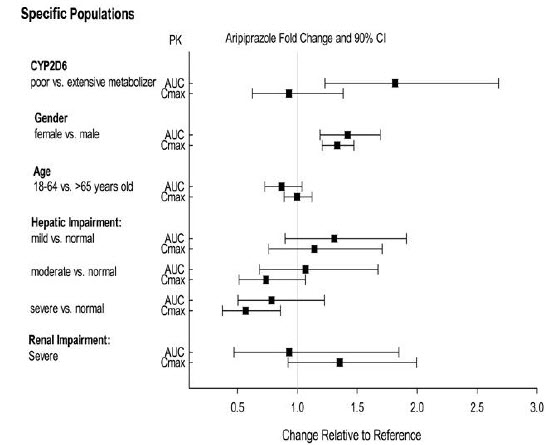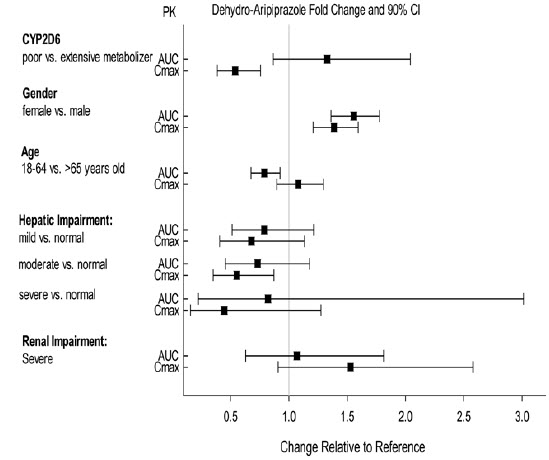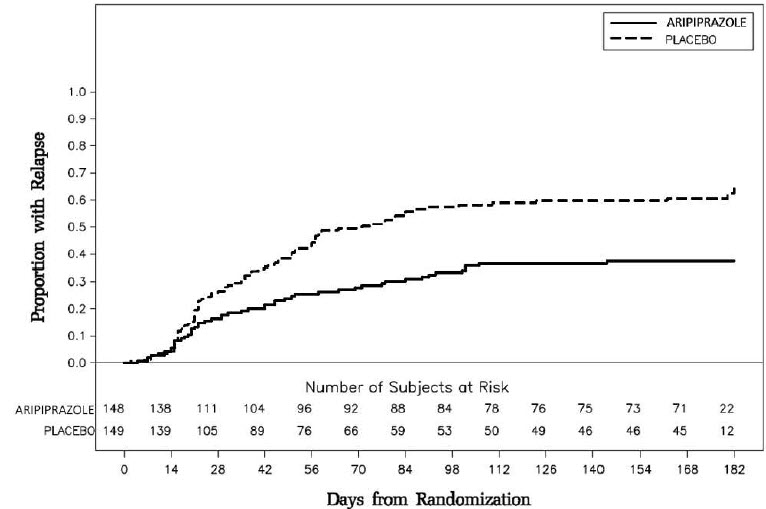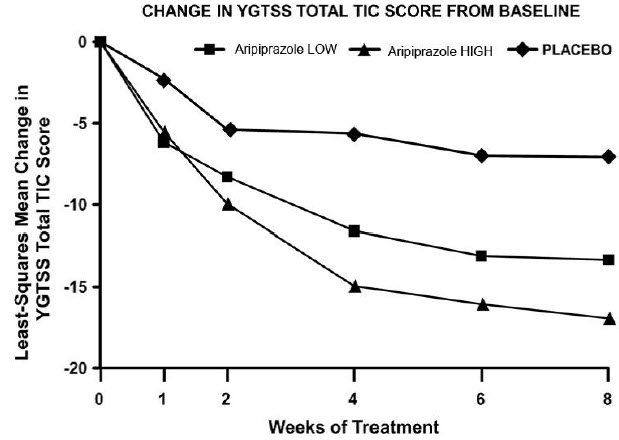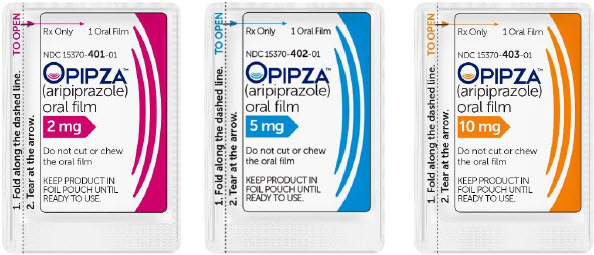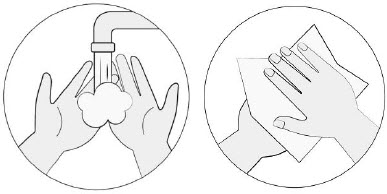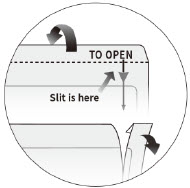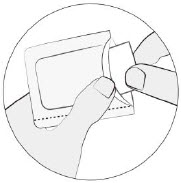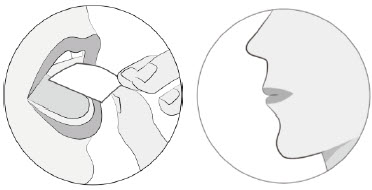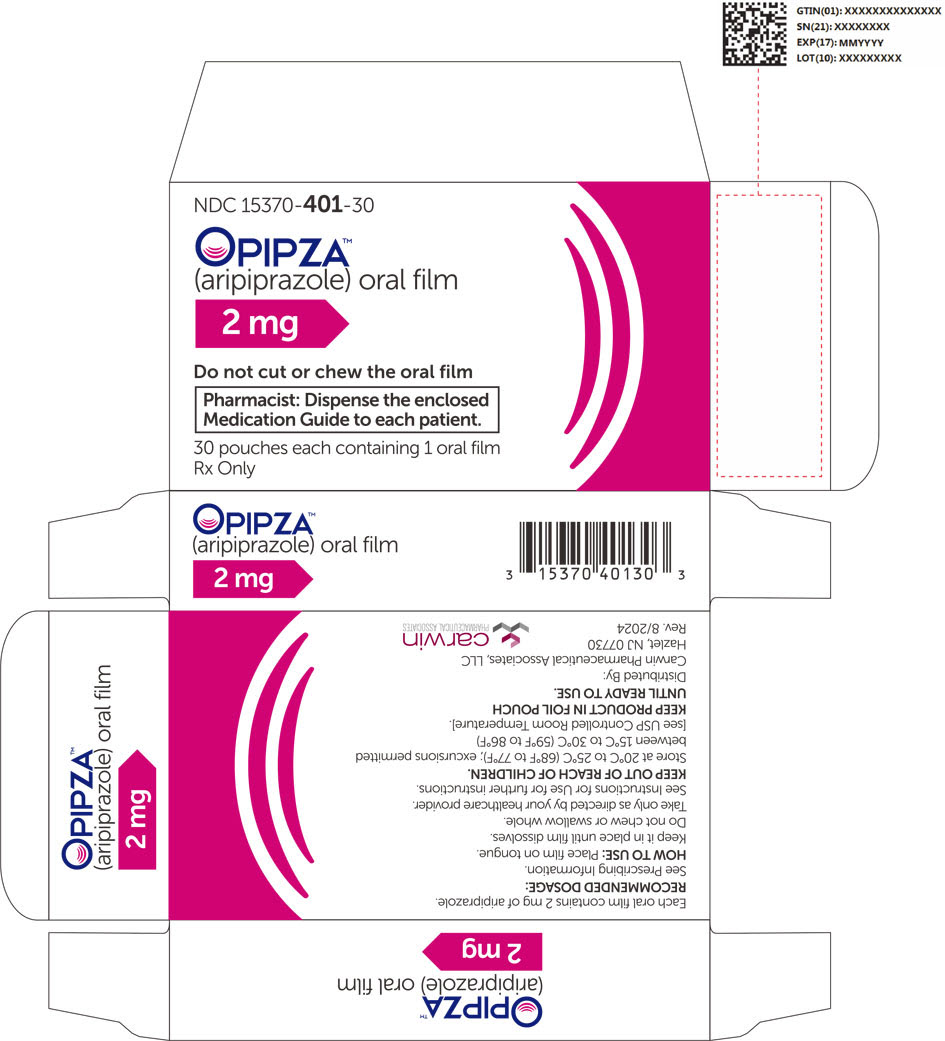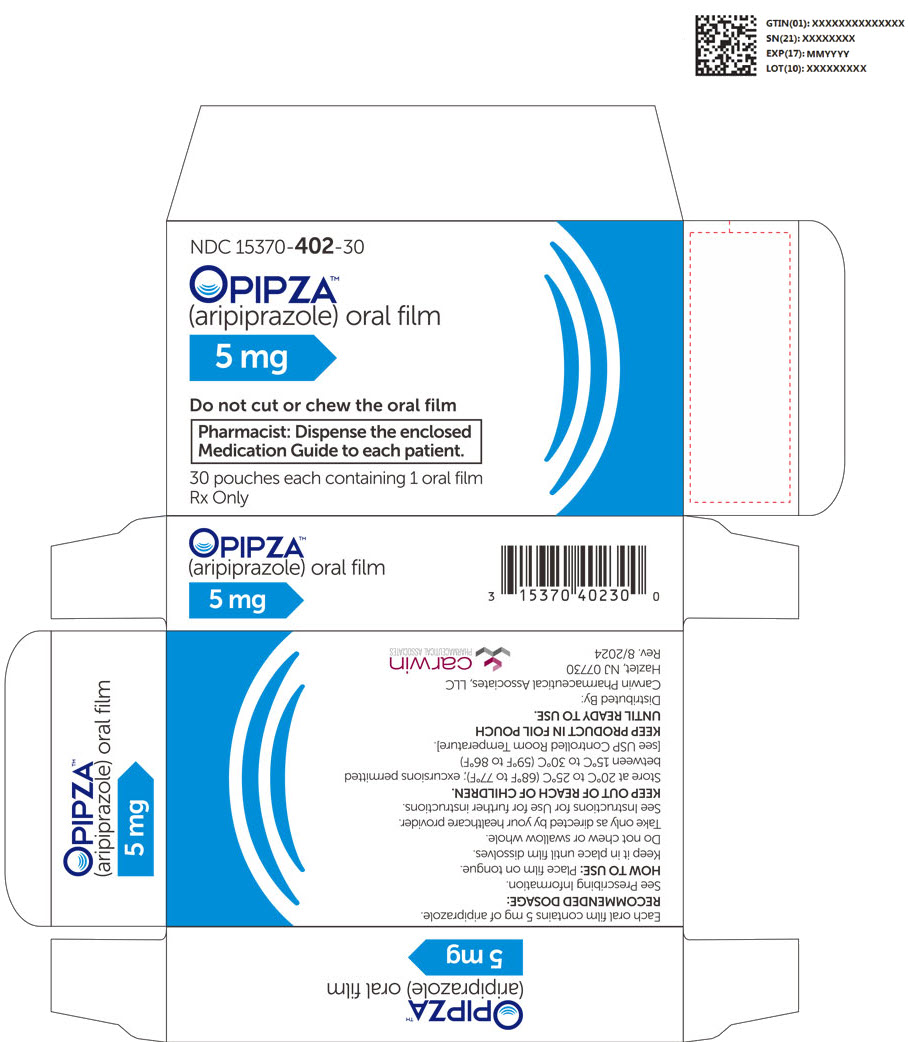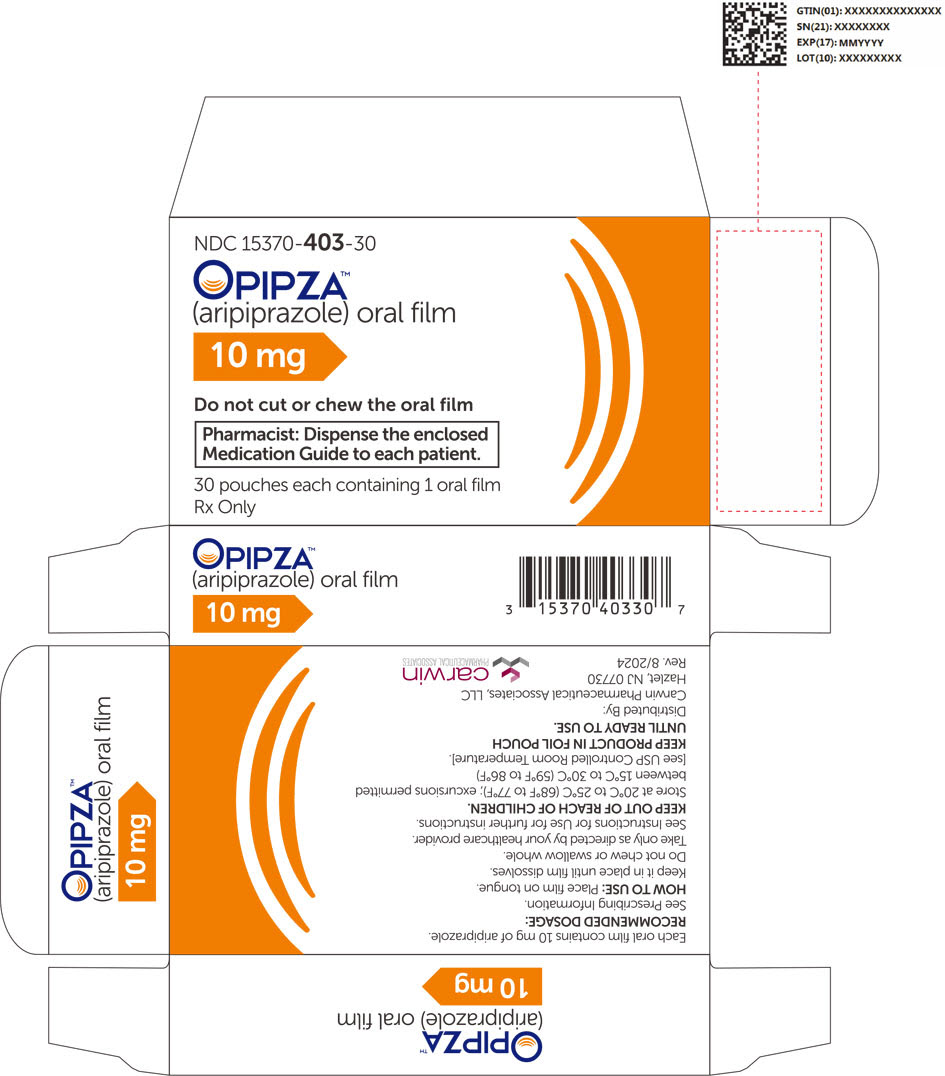 DRUG LABEL: OPIPZA
NDC: 15370-401 | Form: FILM, SOLUBLE
Manufacturer: Carwin Pharmaceutical Associates, LLC
Category: prescription | Type: HUMAN PRESCRIPTION DRUG LABEL
Date: 20250130

ACTIVE INGREDIENTS: ARIPIPRAZOLE 2 mg/1 1
INACTIVE INGREDIENTS: HYDROXYPROPYL CELLULOSE, UNSPECIFIED; SODIUM LAURYL SULFATE; SUCRALOSE; GLYCERIN; FD&C BLUE NO. 1; POLYSORBATE 20; PROPYLENE GLYCOL

HIGHLIGHTS OF PRESCRIBING INFORMATION

These highlights do not include all the information needed to use OPIPZA safely and effectively. See full prescribing information for OPIPZA.
OPIPZA (aripiprazole) oral film
Initial U.S. Approval: 2002

WARNING: INCREASED MORTALITY IN ELDERLY PATIENTS WITH DEMENTIARELATED PSYCHOSIS and SUICIDAL THOUGHTS AND BEHAVIORS

WARNING: INCREASED MORTALITY IN ELDERLY PATIENTS WITH DEMENTIA-RELATED PSYCHOSIS and SUICIDAL THOUGHTS AND BEHAVIORS

See full prescribing information for complete boxed warning.

- Elderly patients with dementia-related psychosis treated with antipsychotic drugs are at an increased risk of death. OPIPZA is not approved for the treatment of patients with dementia-related psychosis. (5.1)
- Increased risk of suicidal thinking and behavior in pediatric and young adult patients taking antidepressants. Closely monitor all antidepressant-treated patients for clinical worsening and emergence of suicidal thoughts and behaviors. (5.3)

1 INDICATIONS AND USAGE

OPIPZA is an atypical antipsychotic indicated for:

- treatment of schizophrenia in patients ages 13 years and older (1)
- adjunctive treatment of major depressive disorder (MDD) in adults (1)
- irritability associated with autistic disorder in pediatric patients 6 years and older (1)
- treatment of Tourette's disorder in pediatric patients 6 years and older (1)

2 DOSAGE AND ADMINISTRATION

 |  | Initial Starting Dosage | Recommended Dosage | Maximum Dosage
Schizophrenia (adults) (2.1) |  | 10 to 15 mg/day | 10 to 15 mg/day | 30 mg/day
Schizophrenia – (pediatric patients 13 years and older) (2.1) |  | 2 mg/day | 10 mg/day | 30 mg/day
Adjunctive Treatment of MDD (adults) (2.2) |  | 2 to 5 mg/day | 5 to 10 mg/day | 15 mg/day
Irritability associated with autistic disorder (pediatric patients 6 years and older) (2.3) |  | 2 mg/day | 5 to 10 mg/day | 15 mg/day
Tourette's disorder (pediatric patients 6 years and older) (2.4) | < 50 kg | 2 mg/day | 5 mg/day | 10 mg/day
Tourette's disorder (pediatric patients 6 years and older) (2.4) | ≥ 50 kg | 2 mg/day | 10 mg/day | 20 mg/day

- Dissolve on top of tongue once daily with or without food (2.4)
- Known CYP2D6 poor metabolizers: Administer half of the recommended dosage (2.6)

3 DOSAGE FORMS AND STRENGTHS

- Oral Film: 2 mg, 5 mg, 10 mg (3)

4 CONTRAINDICATIONS

- Known hypersensitivity to aripiprazole (4)

5 WARNINGS AND PRECAUTIONS

- Cerebrovascular Adverse Reactions in Elderly Patients with Dementia-Related Psychosis: Increased incidence of cerebrovascular adverse reactions (e.g., stroke, transient ischemic attack, including fatalities) (5.2)
- Neuroleptic Malignant Syndrome: Manage with immediate discontinuation and close monitoring (5.4)
- Tardive Dyskinesia: Discontinue if clinically appropriate (5.5)
- Metabolic Changes: Monitor for hyperglycemia/diabetes mellitus, dyslipidemia, and weight gain (5.6)
- Pathological Gambling and Other Compulsive Behaviors: Consider dose reduction or discontinuation (5.7)
- Orthostatic Hypotension and Syncope: Monitor heart rate and blood pressure and caution patients with known cardiovascular or cerebrovascular disease, and risk of dehydration or syncope (5.8)
- Leukopenia, Neutropenia, and Agranulocytosis: Perform complete blood cell counts (CBC) in patients with a history of a clinically significant low white blood cell count (WBC) or a history of leukopenia or neutropenia. Consider discontinuing OPIPZA if clinically significant decline in WBC in the absence of other causative factors (5.10)
- Seizures: Use cautiously in patients with a history of seizures or with conditions that lower the seizure threshold (5.11)
- Potential for Cognitive and Motor Impairment: Use caution when operating machinery (5.12)

6 ADVERSE REACTIONS

Commonly observed adverse reactions (incidence ≥5% and at least twice that for placebo) were (6.1):

- Schizophrenia (adults): akathisia
- Schizophrenia (pediatric patients 13 to 17 years): extrapyramidal disorder, somnolence, and tremor
- Adjunctive treatment of MDD (adults): akathisia, restlessness, insomnia, constipation, fatigue, and blurred vision
- Irritability associated with autistic disorder (pediatric 6 years and older): sedation, fatigue, vomiting, somnolence, tremor, pyrexia, drooling, decreased appetite, salivary hypersecretion, extrapyramidal disorder, and lethargy
- Tourette's disorder (pediatric patients 6 years and older): sedation, somnolence, nausea, headache, nasopharyngitis, fatigue, increased appetite

To report SUSPECTED ADVERSE REACTIONS, contact Carwin Pharmaceutical Associates at 1-877-676-0778 or FDA at 1-800-FDA-1088 or www.fda.gov/medwatch.

7 DRUG INTERACTIONS

Dosage adjustments for patients taking CYP2D6 inhibitors, CYP3A4 inhibitors, or CYP3A4 inducers (7.1):

Factors | Dosage Recommendations
CYP2D6 Poor Metabolizers taking strong CYP3A4 inhibitors (7.1) | Administer a quarter of recommended dosage (2.6)
Strong CYP2D6 or CYP3A4 inhibitors (7.1) | Administer half of recommended dosage (2.6)
Strong CYP2D6 and CYP3A4 inhibitors (7.1) | Administer a quarter of recommended dosage (2.6)
Strong CYP3A4 inducers (7.1) | Double the recommended dosage over 1 to 2 weeks (2.6)

8 USE IN SPECIFIC POPULATIONS

Pregnancy: May cause extrapyramidal and/or withdrawal symptoms in neonates with third trimester exposure (8.1)

FULL PRESCRIBING INFORMATION

WARNING: INCREASED MORTALITY IN ELDERLY PATIENTS WITH DEMENTIARELATED PSYCHOSIS and SUICIDAL THOUGHTS AND BEHAVIORS

Increased Mortality in Elderly Patients with Dementia-Related Psychosis

Elderly patients with dementia-related psychosis treated with antipsychotic drugs are at an increased risk of death.

OPIPZA is not approved for the treatment of patients with dementia-related psychosis [see Warnings and Precautions (5.1)].

Suicidal Thoughts and Behaviors

Antidepressants increased the risk of suicidal thoughts and behavior in pediatric and young adult patients in shortterm studies. Closely monitor all antidepressant-treated patients for clinical worsening, and for emergence of suicidal thoughts and behaviors [see Warnings and Precautions (5.3)].

1 INDICATIONS AND USAGE

OPIPZA is indicated for the:

- treatment of schizophrenia in patients ages 13 years and older
- adjunctive treatment of major depressive disorder (MDD) in adults
- treatment of irritability associated with autistic disorder in pediatric patients 6 years and older
- treatment of Tourette's disorder in pediatric patients 6 years and older

2 DOSAGE AND ADMINISTRATION

2.1 Schizophrenia in Patients 13 Years and Older

Adults

The recommended starting and target dosage of OPIPZA for the treatment of schizophrenia in adults is 10 mg or 15 mg once daily. Aripiprazole has been systematically evaluated and shown to be effective in a dose range of 10 mg to 30 mg per day; however, doses higher than 10 mg or 15 mg per day were not more effective than 10 mg or 15 mg per day. Dosage increases should generally not be made before 2 weeks, the time needed to achieve steady-state [see Clinical Studies (14.2)].

Pediatric Patients Ages 13 Years and Older

The recommended starting dosage of OPIPZA for the treatment of schizophrenia in pediatric patients 13 years and older is 2 mg once daily. The recommended target dosage of OPIPZA is 10 mg once daily. Aripiprazole was studied in pediatric patients 13 to 17 years of age with schizophrenia at daily dosages of 10 mg and 30 mg. The starting daily dosage in these patients was 2 mg, which was titrated to 5 mg after 2 days and to the target dose of 10 mg after 2 additional days. Subsequent dose increases should be administered in 5 mg increments. The 30 mg per day dosage was not shown to be more efficacious than the 10 mg per day dosage.

2.2 Adjunctive Treatment of Major Depressive Disorder in Adults

The recommended starting dosage for OPIPZA as adjunctive treatment of MDD in adults already taking an antidepressant is 2 mg to 5 mg once daily. The recommended dosage range is 2 mg to 15 mg once daily. Dosage adjustments of up to 5 mg per day should occur gradually, at intervals of no less than one week [see Clinical Studies (14.3)]. Patients should be periodically reassessed to determine the continued need for maintenance treatment.

2.3 Irritability Associated with Autistic Disorder in Pediatric Patients 6 years and Older

The recommended dosage range for the treatment of pediatric patients 6 to 17 years with irritability associated with autistic disorder is 5 mg to 15 mg once daily.

Dosing should be initiated at 2 mg once daily. The dose should be increased to 5 mg per day, with subsequent increases to 10 mg or 15 mg per day if needed. Dose adjustments of up to 5 mg per day should occur gradually, at intervals of no less than one week [see Clinical Studies (14.4)]. Patients should be periodically reassessed to determine the continued need for maintenance treatment.

2.4 Tourette's Disorder in Pediatric Patients 6 years and Older

The recommended dosage range for treatment of Tourette's disorder in pediatric patients 6 years and older is 5 mg to 20 mg once daily.

For patients weighing less than 50 kg, dosage should be initiated at 2 mg once daily with a target dosage of 5 mg once daily after 2 days. The dosage can be increased to 10 mg once daily in patients who do not achieve optimal control of tics. Dosage adjustments should occur gradually at intervals of no less than one week.

For patients weighing 50 kg or more, dosing should be initiated at 2 mg once daily for 2 days, and then increased to 5 mg once daily for 5 days, with a target dosage of 10 mg once daily on Day 8. The dosage can be increased up to 20 mg once daily for patients who do not achieve optimal control of tics. Dosage adjustments should occur gradually in increments of 5 mg per day at intervals of no less than one week [see Clinical Studies (14.5)].

Patients should be periodically reassessed to determine the continued need for maintenance treatment.

2.5 Important Administration Information

Instruct patients and/or caregivers to read the "Instruction for Use" carefully for complete directions on how to properly dose and administer OPIPZA.

Administer OPIPZA orally with or without food [see Clinical Pharmacology (12.3)].

Apply OPIPZA on top of the tongue where it dissolves in saliva and can be swallowed in a normal manner without the need for water or other liquids.

The patient should refrain from chewing the film and should not swallow an undissolved film. Do not cut or split OPIPZA.

Administer only one oral film at a time. If an additional film is needed to complete the dosage, administer after the previous film has completely dissolved.

2.6 Dosage Recommendations and Modifications for Cytochrome P450 Considerations

Dosage recommendations and modifications for patients who are known CYP2D6 poor metabolizers and/or in patients taking concomitant CYP3A4 inhibitors, CYP2D6 inhibitors, or strong CYP3A4 inducers are described in Table 1.

When the coadministered drug is withdrawn from the combination therapy, Aripiprazole Oral Film dosage should be adjusted to its previous dose. When the coadministered CYP3A4 inducer is withdrawn, Aripiprazole Oral Film dosage should be reduced to the previous dose over 1 to 2 weeks. Patients receiving a combination of strong, moderate, and weak inhibitors of CYP3A4 and CYP2D6 (e.g., a strong CYP3A4 inhibitor and a moderate CYP2D6 inhibitor or a moderate CYP3A4 inhibitor with a moderate CYP2D6 inhibitor), the dosing may be reduced to one-quarter (25%) of the recommended dose initially and then adjusted to achieve clinical response [see Dosage and Administration (2.5)].

Table 1: Dosage Recommendations and Modifications for OPIPZA in Patients Who are Known CYP2D6 Poor Metabolizers and in Patients Taking Concomitant CYP2D6 Inhibitors and/or 3A4 Inhibitors, CYP3A4 Inducers
Patient Population | Dosage Recommendations and Modifications for OPIPZA
CYP2D6 Poor Metabolizers
Known CYP2D6 Poor Metabolizers | Administer half of the recommended dose
Known CYP2D6 Poor Metabolizers taking concomitant strong CYP3A4 inhibitors | Administer a quarter of the recommended dose
Patients Taking OPIPZA with CYP2D6 Inhibitors and/or CYP3A4 Inhibitors, CYP3A4 Inducers
Concomitant use of OPIPZA with strong CYP2D6 or CYP3A4 inhibitors | Administer half of the recommended dose
Concomitant use of OPIPZA with strong CYP2D6 and CYP3A4 inhibitors | Administer a quarter of the recommended dose
Concomitant use of OPIPZA with strong CYP3A4 inducers | Double the recommended dose over 1 to 2 weeks

When adjunctive OPIPZA is administered to patients with major depressive disorder, OPIPZA should be administered without dosage adjustment as specified in Dosage and Administration (2.2).

3 DOSAGE FORMS AND STRENGTHS

OPIPZA is a rectangular white film in strengths of 2 mg (1 cm by 1.2 cm), 5 mg (2 cm by 1.5 cm), and 10 mg (2 cm by 3 cm) containing the markings A2, A5, and A10, respectively.

4 CONTRAINDICATIONS

OPIPZA is contraindicated in patients with a history of a hypersensitivity to aripiprazole. Hypersensitivity reactions ranging from pruritus/urticaria to anaphylaxis have been reported in patients receiving aripiprazole [see Adverse Reactions (6.1)].

5 WARNINGS AND PRECAUTIONS

5.1 Increased Mortality in Elderly Patients with Dementia-Related Psychosis

Elderly patients with dementia-related psychosis treated with antipsychotic drugs are at an increased risk of death. Analyses of 17 placebo-controlled trials (modal duration of 10 weeks), largely in patients taking atypical antipsychotic drugs, revealed a risk of death in drug-treated patients of between 1.6 to 1.7 times the risk of death in placebo-treated patients. Over the course of a typical 10-week controlled trial, the rate of death in drug-treated patients was about 4.5%, compared to a rate of about 2.6% in the placebo group.

Although the causes of death were varied, most of the deaths appeared to be either cardiovascular (e.g., heart failure, sudden death) or infectious (e.g., pneumonia) in nature. Observational studies suggest that, similar to atypical antipsychotic drugs, treatment with conventional antipsychotic drugs may increase mortality. The extent to which the findings of increased mortality in observational studies may be attributed to the antipsychotic drug as opposed to some characteristic(s) of the patients is not clear.

OPIPZA is not approved for the treatment of patients with dementia-related psychosis [see Boxed Warning and Warnings and Precautions (5.2)]

5.2 Cerebrovascular Adverse Reactions, Including Stroke in Elderly Patients with Dementia-Related Psychosis

In placebo-controlled clinical studies (two flexible dose and one fixed dose study) of dementia-related psychosis, there was an increased incidence of cerebrovascular adverse reactions (e.g., stroke, transient ischemic attack), including fatalities, in aripiprazole-treated patients (mean age: 84 years; range: 78 to 88 years). In the fixed-dose study, there was a statistically significant dose response relationship for cerebrovascular adverse reactions in patients treated with aripiprazole. OPIPZA is not approved for the treatment of patients with dementia-related psychosis [see Warnings and Precautions (5.1)].

5.3 Suicidal Thoughts and Behaviors in Adolescents and Young Adults

In pooled analyses of placebo-controlled trials of antidepressant drugs (SSRIs and other antidepressant classes) that included approximately 77,000 adult patients and 4,500 pediatric patients, the incidence of suicidal thoughts and behaviors in antidepressant-treated patients age 24 years and younger was greater than in placebo-treated patients. There was considerable variation in risk of suicidal thoughts and behaviors among drugs, but there was an increased risk identified in young patients for most drugs studied. There were differences in absolute risk of suicidal thoughts and behaviors across the different indications, with the highest incidence in patients with MDD. The drug-placebo differences in the number of cases of suicidal thoughts and behaviors per 1,000 patients treated are provided in Table 2.

Table 2: Risk Differences of the Number of Patients of Suicidal Thoughts and Behavior in the Pooled Placebo-Controlled Trials of Antidepressants in Pediatric [OPIPZA is not approved in pediatric patients with MDD.] and Adult Patients
Age Range | Drug-Placebo Difference in Number of Patients of Suicidal Thoughts or Behaviors per 1,000 Patients Treated
 | Increases Compared to Placebo
<18 years old | 14 additional patients
18 to 24 years old | 5 additional patients
 | Decreases Compared to Placebo
25 to 64 years old | 1 fewer patient
≥65 years old | 6 fewer patient

It is unknown whether the risk of suicidal thoughts and behaviors in children, adolescents, and young adults extends to longer-term use, i.e., beyond four months. However, there is substantial evidence from placebo-controlled maintenance trials in adults with MDD that antidepressants delay the recurrence of depression and that depression itself is a risk factor for suicidal thoughts and behaviors.

Monitor all antidepressant-treated patients for any indication for clinical worsening and emergence of suicidal thoughts and behaviors, especially during the initial few months of drug therapy, and at times of dosage changes. Counsel family members or caregivers of patients to monitor for changes in behavior and to alert the healthcare provider. Consider changing the therapeutic regimen, including possibly discontinuing OPIPZA, in patients whose depression is persistently worse, or who are experiencing emergent suicidal thoughts or behaviors. It should be noted that OPIPZA is not approved for use in treating depression in the pediatric population.

5.4 Neuroleptic Malignant Syndrome (NMS)

Neuroleptic Malignant Syndrome (NMS), a potentially fatal symptom complex has been reported with antipsychotic drugs, including aripiprazole. Rare cases of NMS have been reported during aripiprazole treatment in the global clinical database.

Clinical manifestations of NMS are hyperpyrexia, muscle rigidity, altered mental status, and evidence of autonomic instability (irregular pulse or blood pressure, tachycardia, diaphoresis, and cardiac dysrhythmia). Additional signs may include elevated creatine phosphokinase, myoglobinuria (rhabdomyolysis), and acute renal failure.

If NMS is suspected, immediately discontinue OPIPZA and provide symptomatic treatment and monitoring.

5.5 Tardive Dyskinesia

Tardive dyskinesia, a syndrome of potentially irreversible, involuntary, dyskinetic movements may develop in patients treated with antipsychotic drugs. Although the prevalence of the syndrome appears to be highest among the elderly, especially elderly women, it is impossible to predict which patients will develop the syndrome. Whether antipsychotic drug products differ in their potential to cause tardive dyskinesia is unknown.

The risk of developing tardive dyskinesia and the likelihood that it will become irreversible appear to increase as the duration of treatment and the total cumulative dose increases. However, the syndrome can develop after relatively brief treatment periods at low doses. It may also occur after discontinuation of treatment.

Tardive dyskinesia may remit, partially or completely, if antipsychotic treatment is discontinued. Antipsychotic treatment, itself may suppress (or partially suppress) the signs and symptoms of the syndrome and may possibly mask the underlying process. The effect that symptomatic suppression has upon the long-term course of the syndrome is unknown.

Given these considerations, OPIPZA should be prescribed in a manner that is most likely to minimize the occurrence of tardive dyskinesia. Chronic antipsychotic treatment should generally be reserved for patients who suffer from a chronic illness that (1) is known to respond to antipsychotic drugs and (2) for whom alternative, equally effective, but potentially less harmful treatments are not available or appropriate. In patients who do require chronic treatment, the smallest dose and the shortest duration of treatment producing a satisfactory clinical response should be sought. The need for continued treatment should be reassessed periodically.

If signs and symptoms of tardive dyskinesia appear in a patient treated with OPIPZA, drug discontinuation should be considered. However, some patients may require treatment with OPIPZA despite the presence of the syndrome.

5.6 Metabolic Changes

Atypical antipsychotic drugs have been associated with metabolic changes that include hyperglycemia/diabetes mellitus, dyslipidemia, and body weight gain. While all drugs in the class have been shown to produce some metabolic changes, each drug has its own specific risk profile.

Hyperglycemia/Diabetes Mellitus

Hyperglycemia, in some cases extreme and associated with diabetic ketoacidosis or hyperosmolar coma or death, have been reported in patients treated with atypical antipsychotics. There have been reports of hyperglycemia in patients treated with aripiprazole [see Adverse Reactions (6.1, 6.2)]. Assessment of the relationship between atypical antipsychotic use and glucose abnormalities is complicated by the possibility of an increased background risk of diabetes mellitus in patients with schizophrenia and the increasing incidence of diabetes mellitus in the general population. Given these confounders, the relationship between atypical antipsychotic use and hyperglycemia-related adverse events is not completely understood. However, epidemiological studies suggest an increased risk of hyperglycemia-related adverse reactions in patients treated with the atypical antipsychotics.

Patients with an established diagnosis of diabetes mellitus who are started on atypical antipsychotics, including OPIPZA, should be monitored regularly for worsening of glucose control. Patients with risk factors for diabetes mellitus (e.g., obesity, family history of diabetes) who are starting treatment with atypical antipsychotics should undergo fasting blood glucose testing at the beginning of treatment and periodically during treatment. Any patient treated with atypical antipsychotics should be monitored for symptoms of hyperglycemia including polydipsia, polyuria, polyphagia, and weakness. Patients who develop symptoms of hyperglycemia during treatment with atypical antipsychotics should undergo fasting blood glucose testing. In some cases, hyperglycemia has resolved when the atypical antipsychotic was discontinued; however, some patients required continuation of anti-diabetic treatment despite discontinuation of the atypical antipsychotic drug.

Adults

In an analysis of 13 placebo-controlled monotherapy trials in adults, primarily with schizophrenia or another indication, the mean change in fasting glucose in aripiprazole-treated patients (+4.4 mg/dL; median exposure 25 days; N=1,057) was not significantly different than in placebo-treated patients (+2.5 mg/dL; median exposure 22 days; N=799). Table 3 shows the proportion of aripiprazole-treated patients with normal and borderline fasting glucose at baseline (median exposure 25 days) that had high fasting glucose measurements compared to placebo-treated patients (median exposure 22 days).

Table 3: Changes in Fasting Glucose from Placebo-Controlled Monotherapy Trials in Adults
 | Category Change (at least once) from Baseline | Treatment Arm | n/N | %
Fasting Glucose | Normal to High (<100 mg/dL to ≥126 mg/dL) | Aripiprazole | 31/822 | 3.8
Fasting Glucose | Normal to High (<100 mg/dL to ≥126 mg/dL) | Placebo | 22/605 | 3.6
Fasting Glucose | Borderline to High (≥100 mg/dL and <126 mg/dL to ≥126 mg/dL) | Aripiprazole | 31/176 | 17.6
Fasting Glucose | Borderline to High (≥100 mg/dL and <126 mg/dL to ≥126 mg/dL) | Placebo | 13/142 | 9.2

At 24 weeks, the mean change in fasting glucose in aripiprazole-treated patients was not significantly different than in placebo-treated patients [+2.2 mg/dL (n=42) and +9.6 mg/dL (n=28), respectively].

The mean change in fasting glucose in adjunctive trials of aripiprazole-treated patients with major depressive disorder (+0.7 mg/dL; median exposure 42 days; N=241) was not significantly different than in placebo-treated patients (+0.8 mg/dL; median exposure 42 days; N=246). Table 4 shows the proportion of adult patients with changes in fasting glucose levels from two placebo-controlled, adjunctive trials (median exposure 42 days) in patients with major depressive disorder.

Table 4: Changes in Fasting Glucose from Placebo-Controlled Adjunctive Trials in Adults with Major Depressive Disorder
 | Category Change (at least once) from Baseline | Treatment Arm | n/N | %
Fasting Glucose | Normal to High (<100 mg/dL to ≥126 mg/dL) | Aripiprazole | 2/201 | 1.0
Fasting Glucose | Normal to High (<100 mg/dL to ≥126 mg/dL) | Placebo | 2/204 | 1.0
Fasting Glucose | Borderline to High (≥100 mg/dL and <126 mg/dL to ≥126 mg/dL) | Aripiprazole | 4/34 | 11.8
Fasting Glucose | Borderline to High (≥100 mg/dL and <126 mg/dL to ≥126 mg/dL) | Placebo | 3/37 | 8.1

Pediatric Patients 13 Years and Older

In an analysis of two placebo-controlled trials in pediatric patients 13 to 17 years with schizophrenia and pediatric patients 10 to 17 years with another indication, the mean change in fasting glucose in aripiprazole-treated patients (+4.8 mg/dL; with a median exposure of 43 days; N=259) was not significantly different than in placebo-treated patients (+1.7 mg/dL; with a median exposure of 42 days; N=123).

In an analysis of two placebo-controlled trials in pediatric patients 6 to 17 years with irritability associated with autistic disorder (6 to 17 years) with median exposure of 56 days, the mean change in fasting glucose in aripiprazole-treated patients (–0.2 mg/dL; N=83) was not significantly different than in placebo-treated patients (–0.6 mg/dL; N=33).

In an analysis of two placebo-controlled trials in pediatric patients 6 to 18 years with Tourette's disorder with median exposure of 57 days, the mean change in fasting glucose in aripiprazole-treated patients (0.79 mg/dL; N=90) was not significantly different than in placebo-treated patients (–1.66 mg/dL; N=58).

Table 5 shows the proportion of patients with changes in fasting glucose levels from the pooled pediatric patients (13 to 17 years) with schizophrenia and pediatric patients (10 to 17 years) with another indication (median exposure of 42 to 43 days), from two placebo-controlled trials in pediatric patients (6 to 17 years) with irritability associated with autistic disorder (median exposure of 56 days), and from the two placebo-controlled trials in pediatric patients (6 to 18 years) with Tourette's disorder (median exposure 57 days).

Table 5: Changes in Fasting Glucose from Placebo-Controlled Trials in Pediatric Patients 6 to 17 Years
Category Change (at least once) from Baseline | Indication | Treatment Arm | n/N | %
Fasting Glucose Normal to High (<100 mg/dL to ≥126 mg/dL) | Pooled Schizophrenia and another indication | Aripiprazole | 2/236 | 0.8
Fasting Glucose Normal to High (<100 mg/dL to ≥126 mg/dL) | Pooled Schizophrenia and another indication | Placebo | 2/110 | 1.8
Fasting Glucose Normal to High (<100 mg/dL to ≥126 mg/dL) | Irritability Associated with Autistic Disorder | Aripiprazole | 0/73 | 0
Fasting Glucose Normal to High (<100 mg/dL to ≥126 mg/dL) | Irritability Associated with Autistic Disorder | Placebo | 0/32 | 0
Fasting Glucose Normal to High (<100 mg/dL to ≥126 mg/dL) | Tourette's Disorder | Aripiprazole | 3/88 | 3.4
Fasting Glucose Normal to High (<100 mg/dL to ≥126 mg/dL) | Tourette's Disorder | Placebo | 1/58 | 1.7
Fasting Glucose Borderline to High (≥100 mg/dL and <126 mg/dL to ≥126 mg/dL) | Pooled Schizophrenia and another indication | Aripiprazole | 1/22 | 4.5
Fasting Glucose Borderline to High (≥100 mg/dL and <126 mg/dL to ≥126 mg/dL) | Pooled Schizophrenia and another indication | Placebo | 0/12 | 0
Fasting Glucose Borderline to High (≥100 mg/dL and <126 mg/dL to ≥126 mg/dL) | Irritability Associated with Autistic Disorder | Aripiprazole | 0/9 | 0
Fasting Glucose Borderline to High (≥100 mg/dL and <126 mg/dL to ≥126 mg/dL) | Irritability Associated with Autistic Disorder | Placebo | 0/1 | 0
Fasting Glucose Borderline to High (≥100 mg/dL and <126 mg/dL to ≥126 mg/dL) | Tourette's Disorder | Aripiprazole | 0/11 | 0
Fasting Glucose Borderline to High (≥100 mg/dL and <126 mg/dL to ≥126 mg/dL) | Tourette's Disorder | Placebo | 0/4 | 0

In the pooled trials that enrolled pediatric patients 13 to 17 years with schizophrenia and another indication, the mean change in fasting glucose in aripiprazole-treated patients at 12 weeks was not significantly different than in placebotreated patients [+2.4 mg/dL (n=81) and +0.1 mg/dL (n=15), respectively].

Dyslipidemia

Undesirable alterations in lipids have been observed in patients treated with atypical antipsychotics.

There were no significant differences between aripiprazole-treated patients and patients treated with placebo in the proportion with changes from normal to clinically significant levels for fasting/nonfasting total cholesterol, fasting triglycerides, fasting LDLs, and fasting/nonfasting HDLs. Analyses of patients with at least 12 or 24 weeks of exposure were limited by small numbers of patients.

Adults

Table 6 shows the proportion of adult patients, primarily from pooled schizophrenia and another indication monotherapy placebo-controlled trials, with changes in total cholesterol (pooled from 17 trials; median exposure 21 to 25 days), fasting triglycerides (pooled from eight trials; median exposure 42 days), fasting LDL cholesterol (pooled from eight trials; median exposure 39 to 45 days, except for placebo-treated patients with baseline normal fasting LDL measurements, who had median treatment exposure of 24 days) and HDL cholesterol (pooled from nine trials; median exposure 40 to 42 days).

Table 6: Changes in Blood Lipid Parameters from Placebo-Controlled Monotherapy Trials in Adults
 | Treatment Arm | n/N | %
Total Cholesterol Normal to High (<200 mg/dL to ≥240 mg/dL) | Aripiprazole | 34/1,357 | 2.5
Total Cholesterol Normal to High (<200 mg/dL to ≥240 mg/dL) | Placebo | 27/973 | 2.8
Fasting Triglycerides Normal to High (<150 mg/dL to ≥200 mg/dL) | Aripiprazole | 40/539 | 7.4
Fasting Triglycerides Normal to High (<150 mg/dL to ≥200 mg/dL) | Placebo | 30/431 | 7.0
Fasting LDL Cholesterol Normal to High (<100 mg/dL to ≥160 mg/dL) | Aripiprazole | 2/332 | 0.6
Fasting LDL Cholesterol Normal to High (<100 mg/dL to ≥160 mg/dL) | Placebo | 2/268 | 0.7
HDL Cholesterol Normal to Low (≥40 mg/dL to <40 mg/dL) | Aripiprazole | 121/1,066 | 11.4
HDL Cholesterol Normal to Low (≥40 mg/dL to <40 mg/dL) | Placebo | 99/794 | 12.5

In monotherapy trials in adults, the proportion of patients at 12 weeks and 24 weeks with changes from Normal to High in total cholesterol (fasting/nonfasting), fasting triglycerides, and fasting LDL cholesterol were similar between aripiprazole - and placebo-treated patients: at 12 weeks, Total Cholesterol (fasting/nonfasting), 1/71 (1.4%) vs. 3/74 (4.1%); Fasting Triglycerides, 8/62 (12.9%) vs. 5/37 (13.5%); Fasting LDL Cholesterol, 0/34 (0%) vs. 1/25 (4.0%), respectively; and at 24 weeks, Total Cholesterol (fasting/nonfasting), 1/42 (2.4%) vs. 3/37 (8.1%); Fasting Triglycerides, 5/34 (14.7%) vs. 5/20 (25%); Fasting LDL Cholesterol, 0/22 (0%) vs. 1/18 (5.6%), respectively.

Table 7 shows the proportion of patients with changes in total cholesterol (fasting/nonfasting), fasting triglycerides, fasting LDL cholesterol, and HDL cholesterol from two placebo-controlled adjunctive trials in adults with major depressive disorder (median exposure 42 days).

Table 7: Changes in Blood Lipid Parameters from Placebo-Controlled Adjunctive Trials in Adults with Major Depressive Disorder
 | Treatment Arm | n/N | %
Total Cholesterol Normal to High (<200 mg/dL to ≥240 mg/dL) | Aripiprazole | 3/139 | 2.2
Total Cholesterol Normal to High (<200 mg/dL to ≥240 mg/dL) | Placebo | 7/135 | 5.2
Fasting Triglycerides Normal to High (<150 mg/dL to ≥200 mg/dL) | Aripiprazole | 14/145 | 9.7
Fasting Triglycerides Normal to High (<150 mg/dL to ≥200 mg/dL) | Placebo | 6/147 | 4.1
Fasting LDL Cholesterol Normal to High (<100 mg/dL to ≥160 mg/dL) | Aripiprazole | 0/54 | 0
Fasting LDL Cholesterol Normal to High (<100 mg/dL to ≥160 mg/dL) | Placebo | 0/73 | 0
HDL Cholesterol Normal to Low (≥40 mg/dL to <40 mg/dL) | Aripiprazole | 17/318 | 5.3
HDL Cholesterol Normal to Low (≥40 mg/dL to <40 mg/dL) | Placebo | 10/286 | 3.5

Pediatric Patients 10 to 17 Years

Table 8 shows the proportion of pediatric patients (13 to 17 years) with schizophrenia and pediatric patients (10 to 17 years) with another indication with changes in total cholesterol and HDL cholesterol (pooled from two placebo-controlled trials; median exposure 42 to 43 days) and fasting triglycerides (pooled from two placebo-controlled trials; median exposure 42 to 44 days).

Table 8: Changes in Blood Lipid Parameters from Placebo-Controlled Monotherapy Trials in Pediatric Patients 10 to 17 Years with Schizophrenia and another Indication
 | Treatment Arm | n/N | %
Total Cholesterol Normal to High (<170 mg/dL to ≥200 mg/dL) | Aripiprazole | 3/220 | 1.4
Total Cholesterol Normal to High (<170 mg/dL to ≥200 mg/dL) | Placebo | 0/116 | 0
Fasting Triglycerides Normal to High (<150 mg/dL to ≥200 mg/dL) | Aripiprazole | 7/187 | 3.7
Fasting Triglycerides Normal to High (<150 mg/dL to ≥200 mg/dL) | Placebo | 4/85 | 4.7
HDL Cholesterol Normal to Low (≥40 mg/dL to <40 mg/dL) | Aripiprazole | 27/236 | 11.4
HDL Cholesterol Normal to Low (≥40 mg/dL to <40 mg/dL) | Placebo | 22/109 | 20.2

In monotherapy trials of pediatric patients with schizophrenia and pediatric patients with another indication, the proportion of patients at 12 weeks and 24 weeks with changes from Normal to High in total cholesterol (fasting/nonfasting), fasting triglycerides, and fasting LDL cholesterol were similar between aripiprazole- and placebotreated patients: at 12 weeks, Total Cholesterol (fasting/nonfasting), 0/57 (0%) vs. 0/15 (0%); Fasting Triglycerides, 2/72 (2.8%) vs. 1/14 (7.1%), respectively; and at 24 weeks, Total Cholesterol (fasting/nonfasting), 0/36 (0%) vs. 0/12 (0%); Fasting Triglycerides, 1/47 (2.1%) vs. 1/10 (10.0%), respectively.

Table 9 shows the proportion of patients with changes in total cholesterol (fasting/nonfasting) and fasting triglycerides (median exposure 56 days) and HDL cholesterol (median exposure 55 to 56 days) from two placebo-controlled trials in pediatric patients (6 to 17 years) with irritability associated with autistic disorder.

Table 9: Changes in Blood Lipid Parameters from Placebo-Controlled Trials in Pediatric Patients 6 to 17 Years with Autistic Disorder
 | Treatment Arm | n/N | %
Total Cholesterol Normal to High (<170 mg/dL to ≥200 mg/dL) | Aripiprazole | 1/95 | 1.1
Total Cholesterol Normal to High (<170 mg/dL to ≥200 mg/dL) | Placebo | 0/34 | 0
Fasting Triglycerides Normal to High (<150 mg/dL to ≥200 mg/dL) | Aripiprazole | 0/75 | 0
Fasting Triglycerides Normal to High (<150 mg/dL to ≥200 mg/dL) | Placebo | 0/30 | 0
HDL Cholesterol Normal to Low (≥40 mg/dL to <40 mg/dL) | Aripiprazole | 9/107 | 8.4
HDL Cholesterol Normal to Low (≥40 mg/dL to <40 mg/dL) | Placebo | 5/49 | 10.2

Table 10 shows the proportion of patients with changes in total cholesterol (fasting/nonfasting) and fasting triglycerides (median exposure 57 days) and HDL cholesterol (median exposure 57 days) from two placebo-controlled trials in pediatric patients (6 to 18 years) with Tourette's disorder.

Table 10: Changes in Blood Lipid Parameters from Placebo-Controlled Trials in Pediatric Patients 6 to 18 Years with Tourette's Disorder
 | Treatment Arm | n/N | %
Total Cholesterol Normal to High (<170 mg/dL to ⩾200 mg/dL) | Aripiprazole | 1/85 | 1.2
Total Cholesterol Normal to High (<170 mg/dL to ⩾200 mg/dL) | Placebo | 0/46 | 0
Fasting Triglycerides Normal to High (<150 mg/dL to ⩾200 mg/dL) | Aripiprazole | 5/94 | 5.3
Fasting Triglycerides Normal to High (<150 mg/dL to ⩾200 mg/dL) | Placebo | 2/55 | 3.6
HDL Cholesterol Normal to Low (⩾40 mg/dL to <40 mg/dL) | Aripiprazole | 4/108 | 3.7
HDL Cholesterol Normal to Low (⩾40 mg/dL to <40 mg/dL) | Placebo | 2/67 | 3.0

Weight Gain

Weight gain has been observed with atypical antipsychotic use. Clinical monitoring of weight is recommended.

Adults

In an analysis of 13 placebo-controlled monotherapy trials, primarily from pooled schizophrenia and another indication, with a median exposure of 21 to 25 days, the mean change in body weight in aripiprazole-treated patients was +0.3 kg (N=1673) compared to -0.1 kg (N=1100) in placebo-controlled patients. At 24 weeks, the mean change from baseline in body weight in aripiprazole-treated patients was -1.5 kg (n=73) compared to -0.2 kg (n=46) in patients treated with placebo patients.

In the trials adding aripiprazole to antidepressants, patients first received 8 weeks of antidepressant treatment followed by 6 weeks of adjunctive aripiprazole or placebo in addition to their ongoing antidepressant treatment. The mean change in body weight in patients receiving adjunctive aripiprazole was +1.7 kg (N=347) compared to +0.4 kg (N=330) in patients receiving adjunctive placebo.

Table 11 shows the percentage of adult patients with weight gain ≥7% of body weight by indication.

Table 11: Percentage of Patients from Placebo-Controlled Trials in Adults with Weight Gain ≥7% of Body Weight
 | Indication | Treatment Arm | N | Patients n (%)
Weight gain ≥7% of body weight | Schizophrenia [4 to 6 weeks duration;] | Aripiprazole | 852 | 69 (8.1)
Weight gain ≥7% of body weight | Schizophrenia [4 to 6 weeks duration;] | Placebo | 379 | 12 (3.2)
Weight gain ≥7% of body weight | Another indication [3 weeks duration;] | Aripiprazole | 719 | 16 (2.2)
Weight gain ≥7% of body weight | Another indication [3 weeks duration;] | Placebo | 598 | 16 (2.7)
Weight gain ≥7% of body weight | Major Depressive Disorder (Adjunctive Therapy) [6 weeks duration.] | Aripiprazole | 347 | 18 (5.2)
Weight gain ≥7% of body weight | Major Depressive Disorder (Adjunctive Therapy) [6 weeks duration.] | Placebo | 330 | 2 (0.6)

Pediatric Patients 6 to 17 Years

In an analysis of two placebo-controlled trials in pediatric patients 13 to 17 years with schizophrenia and pediatric patients 10 to 17 years with another indication with median exposure of 42 to 43 days, the mean change in body weight in aripiprazole-treated patients was +1.6 kg (N=381) compared to +0.3 kg (N=187) in placebo-treated patients. At 24 weeks, the mean change from baseline in body weight in aripiprazole-treated patients was +5.8 kg (n=62) compared to +1.4 kg (n=13) in patients treated with placebo.

In two short-term, placebo-controlled trials in pediatric patients (6 to 17 years) with irritability associated with autistic disorder with median exposure of 56 days, the mean change in body weight in aripiprazole-treated patients was +1.6 kg (n=209) compared to +0.4 kg (n=98) in pediatric patients treated with placebo.

In two short-term, placebo-controlled trials in pediatric patients 6 to 18 years with Tourette's disorder with median exposure of 57 days, the mean change in body weight in aripiprazole-treated patients was +1.5 kg (n=105) compared to +0.4 kg (n=66) in patients treated with placebo.

Table 12 shows the percentage of pediatric patients (6 to 17 years) with weight gain ≥7% of body weight by indication.

Table 12: Percentage of Patients from Placebo-Controlled Monotherapy Trials in Pediatric Patients 6 to 17 Years with Weight Gain ≥7% of Body Weight
 | Indication | Treatment Arm | N | Patients n (%)
Weight gain ≥7% of body weight | Pooled Schizophrenia and another indication [4 to 6 weeks duration;] | Aripiprazole | 381 | 20 (5.2)
Weight gain ≥7% of body weight | Pooled Schizophrenia and another indication [4 to 6 weeks duration;] | Placebo | 187 | 3 (1.6)
Weight gain ≥7% of body weight | Irritability Associated with Autistic Disorder [8 weeks duration;] | Aripiprazole | 209 | 55 (26.3)
Weight gain ≥7% of body weight | Irritability Associated with Autistic Disorder [8 weeks duration;] | Placebo | 98 | 7 (7.1)
Weight gain ≥7% of body weight | Tourette's Disorder [8 to 10 weeks duration.] | Aripiprazole | 105 | 21 (20.0)
Weight gain ≥7% of body weight | Tourette's Disorder [8 to 10 weeks duration.] | Placebo | 66 | 5 (7.6)

In an open-label trial that enrolled patients from the two placebo-controlled trials of pediatric patients 13 to 17 years with schizophrenia and pediatric patients 10 to 17 years with another indication, 73.2% of patients (238/325) completed 26 weeks of therapy with aripiprazole. After 26 weeks, 32.8% of patients gained ≥7% of their body weight, not adjusted for normal growth. To adjust for normal growth, z-scores were derived (measured in standard deviations [SD]), which normalize for the natural growth of pediatric patients and adolescents by comparisons to age- and gender-matched population standards. A z-score change <0.5 SD is considered not clinically significant. After 26 weeks, the mean change in z-score was 0.09 SD.

In an open-label trial that enrolled patients from two short-term, placebo-controlled trials, pediatric patients 6 to 17 years with irritability associated with autistic disorder, as well as de novo patients, 60.3% (199/330) completed one year of therapy with aripiprazole. The mean change in weight z-score was 0.26 SDs for patients receiving >9 months of treatment.

When treating pediatric patients for any indication, weight gain should be monitored and assessed against that expected for normal growth.

5.7 Pathological Gambling and Other Compulsive Behaviors

Post-marketing case reports suggest that patients can experience intense urges, particularly for gambling, and the inability to control these urges while taking aripiprazole. Other compulsive urges, reported less frequently, include sexual urges, shopping, eating or binge eating, and other impulsive or compulsive behaviors. Because patients may not recognize these behaviors as abnormal, it is important for prescribers to ask patients or their caregivers specifically about the development of new or intense gambling urges, compulsive sexual urges, compulsive shopping, binge or compulsive eating, or other urges while being treated with aripiprazole. It should be noted that impulse-control symptoms can be associated with the underlying disorder. In some cases, although not all, urges were reported to have stopped when the dose was reduced, or the medication was discontinued. Compulsive behaviors may result in harm to the patient and others if not recognized. Consider dose reduction or stopping the medication if a patient develops such urges.

5.8 Orthostatic Hypotension and Syncope

OPIPZA may cause orthostatic hypotension, perhaps due to its α1-adrenergic receptor antagonism. The incidence of orthostatic hypotension-associated events from short-term, placebo-controlled trials of adult patients treated with another oral aripiprazole product (n=2,467) included (aripiprazole incidence, placebo incidence) orthostatic hypotension (1%, 0.3%), postural dizziness (0.5%, 0.3%), and syncope (0.5%, 0.4%); of pediatric patients 6 to 18 years of age (n=732) on another oral aripiprazole product included orthostatic hypotension (0.5%, 0%), postural dizziness (0.4%, 0%), and syncope (0.2%, 0%) [see Adverse Reactions (6.1)].

The incidence of a significant orthostatic change in blood pressure (defined as a decrease in systolic blood pressure ≥20 mmHg accompanied by an increase in heart rate ≥25 bpm when comparing standing to supine values) for another oral aripiprazole product was not meaningfully different from placebo (aripiprazole incidence, placebo incidence): in adults treated with another oral aripiprazole product (4%, 2%), in pediatric patients treated with another oral aripiprazole-product aged 6 to 18 years (0.4%, 1%).

Use OPIPZA with caution in patients with known cardiovascular disease (history of myocardial infarction or ischemic heart disease, heart failure or conduction abnormalities), cerebrovascular disease, or conditions which would predispose patients to hypotension (dehydration, hypovolemia, and treatment with antihypertensive medications) [see Drug Interactions (7.1)]. Monitoring of orthostatic vital signs should be considered in patients who are vulnerable to hypotension.

5.9 Falls

Antipsychotics, including OPIPZA, may cause somnolence, postural hypotension, motor and sensory instability, which may lead to falls and, consequently, fractures or other injuries. For patients with diseases, conditions, or medications that could exacerbate these effects, complete fall risk assessments when initiating antipsychotic treatment and recurrently for patients on long-term antipsychotic therapy.

5.10 Leukopenia, Neutropenia, and Agranulocytosis

In clinical trials and/or postmarketing experience, events of leukopenia and neutropenia have been reported temporally related to antipsychotic agents, including aripiprazole. Agranulocytosis has also been reported.

Possible risk factors for leukopenia/neutropenia include pre-existing low white blood cell count (WBC)/absolute neutrophil count (ANC) and history of drug-induced leukopenia/neutropenia. In patients with a history of a clinically significant low WBC/ANC or drug-induced leukopenia/neutropenia, perform a complete blood count (CBC) frequently during the first few months of therapy. In such patients, consider discontinuation of OPIPZA at the first sign of a clinically significant decline in WBC in the absence of other causative factors.

Monitor patients with clinically significant neutropenia for fever or other symptoms or signs of infection and treat promptly if such symptoms or signs occur. Discontinue OPIPZA in patients with severe neutropenia (absolute neutrophil count <1,000/mm^3) and follow their WBC counts until recovery.

5.11 Seizures

In short-term, placebo-controlled trials, patients with a history of seizures excluded seizures/convulsions occurred in 0.1% (3/2,467) of undiagnosed adult patients and in 0.1% (1/732) of pediatric patients (6 to 18 years) treated with another oral aripiprazole product.

As with other antipsychotic drugs, use OPIPZA cautiously in patients with a history of seizures or with conditions that lower the seizure threshold. Conditions that lower the seizure threshold may be more prevalent in a population of 65 years or older.

5.12 Potential for Cognitive and Motor Impairment

OPIPZA, like other antipsychotics, may have the potential to impair judgment, thinking, or motor skills. For example, in short-term, placebo-controlled trials of another oral aripiprazole product, somnolence (including sedation) was reported as follows (aripiprazole incidence, placebo incidence): in adult patients (n=2,467) treated with oral aripiprazole (11%, 6%), in pediatric patients ages 6 to 17 years (n=611) (24%, 6%). Somnolence (including sedation) led to discontinuation in 0.3% (8/2,467) of adult patients and 3% (20/732) of pediatric patients (6 to 18 years) on oral aripiprazole in short-term, placebo-controlled trials.

Patients should be cautioned about operating hazardous machinery or operating a motor vehicle, until they are reasonably certain that therapy with OPIPZA does not affect them adversely.

5.13 Body Temperature Regulation

Disruption of the body's ability to reduce core body temperature has been attributed to antipsychotic agents. Appropriate care is advised when prescribing OPIPZA for patients who will be experiencing conditions which may contribute to an elevation in core body temperature, (e.g., exercising strenuously, exposure to extreme heat, receiving concomitant medication with anticholinergic activity, or being subject to dehydration) [see Adverse Reactions (6.2)].

5.14 Dysphagia

Esophageal dysmotility and aspiration have been associated with antipsychotic drug use, including aripiprazole. OPIPZA and other antipsychotic drugs should be used cautiously in patients at risk for aspiration pneumonia [see Warnings and Precautions (5.1) and Adverse Reactions (6.2)].

6 ADVERSE REACTIONS

The following adverse reactions are discussed in more detail in other sections of the labeling:

- Increased Mortality in Elderly Patients with Dementia-Related Psychosis [see Boxed Warning and Warnings and Precautions (5.1)]
- Cerebrovascular Adverse Reactions, Including Stroke in Elderly Patients with Dementia-Related Psychosis [see Warnings and Precautions (5.2)]
- Suicidal Thoughts and Behaviors in Children, Adolescents, and Young Adults [see Boxed Warning and Warnings and Precautions (5.3)]
- Neuroleptic Malignant Syndrome (NMS) [see Warnings and Precautions (5.4)]
- Tardive Dyskinesia [see Warnings and Precautions (5.5)]
- Metabolic Changes [see Warnings and Precautions (5.6)]
- Pathological Gambling and Other Compulsive Behaviors [see Warnings and Precautions (5.7)]
- Orthostatic Hypotension [see Warnings and Precautions (5.8)]
- Falls [see Warnings and Precautions (5.9)]
- Leukopenia, Neutropenia, and Agranulocytosis [see Warnings and Precautions (5.10)]
- Seizures [see Warnings and Precautions (5.11)]
- Potential for Cognitive and Motor Impairment [see Warnings and Precautions (5.12)]
- Body Temperature Regulation [see Warnings and Precautions (5.13)]
- Dysphagia [see Warnings and Precautions (5.14)]

6.1 Clinical Trials Experience

Because clinical trials are conducted under widely varying conditions, adverse reaction rates observed in the clinical trials of a drug cannot be directly compared to rates in the clinical trials of another drug and may not reflect the rates observed in practice.

The safety of OPIPZA for the treatment of adults with schizophrenia in patients 13 years and older, adjunctive treatment of adults with MDD, treatment of irritability associated with autistic disorder in pediatric patients 6 years and older, and treatment of Tourette's disorder in pediatric patients 6 years and older is based on adequate and well-controlled studies of another oral aripiprazole product. Below is a display of adverse reactions of oral aripiprazole (referred to as "aripiprazole" in this section) from those adequate and well-controlled studies.

Aripiprazole has been evaluated for safety in 13,543 adult patients who participated in multiple-dose, clinical trials in schizophrenia, major depressive disorder, and other indications, and who had approximately 7,619 patient-years of exposure to oral aripiprazole. A total of 3,390 patients were treated with oral aripiprazole for at least 180 days and 1,933 patients treated with oral aripiprazole had at least one year of exposure.

Aripiprazole has been evaluated for safety in 1,686 pediatric patients (6 to 18 years) who participated in multiple-dose, clinical trials in schizophrenia, autistic disorder, Tourette's disorder or other indications who had approximately 1,342 patient-years of exposure to oral aripiprazole. A total of 959 pediatric patients were treated with oral aripiprazole for at least 180 days and 556 pediatric patients treated with oral aripiprazole had at least one year of exposure.

The conditions and duration of treatment with aripiprazole (monotherapy and adjunctive therapy with antidepressants or mood stabilizers) included (in overlapping categories) double-blind, comparative and noncomparative open-label studies, inpatient and outpatient studies, fixed- and flexible-dose studies, and short- and longer-term exposure.

The most common adverse reactions of aripiprazole in adult patients in clinical trials (≥10%) were nausea, vomiting, constipation, headache, dizziness, akathisia, anxiety, insomnia, and restlessness.

The most common adverse reactions of aripiprazole in the pediatric clinical trials (≥10%) were somnolence, headache, vomiting, extrapyramidal disorder, fatigue, increased appetite, insomnia, nausea, nasopharyngitis, and weight increased.

Adverse Reactions in Adult Patients with Schizophrenia

The following findings are based on a pool of five placebo-controlled trials (four 4 week and one 6 week) in which oral aripiprazole was administered in doses ranging from 2 mg/day to 30 mg/day.

The commonly observed adverse reaction associated with the use of aripiprazole in patients with schizophrenia (incidence of 5% or greater and aripiprazole incidence at least twice that for placebo) was akathisia (aripiprazole 8%; placebo 4%).

Table 13 enumerates the pooled incidence, rounded to the nearest percent, of adverse reactions that occurred during acute therapy (up to 6 weeks in schizophrenia and up to 3 weeks in another indication), including only those reactions that occurred in 2% or more of patients treated with aripiprazole (doses ≥2 mg/day) and for which the incidence in patients treated with aripiprazole was greater than the incidence in patients treated with placebo in the combined dataset.

Table 13: Adverse Reactions in Short-Term, Placebo-Controlled Trials in Adult Patients Treated with Oral Aripiprazole
 | Percentage of Patients Reporting Reaction [Adverse reactions reported by at least 2% of patients treated with oral aripiprazole, except adverse reactions which had an incidence equal to or less than placebo.]
Preferred Term | Aripiprazole (n=1,843) | Placebo (n=1,166)
Eye Disorders
Blurred Vision | 3 | 1
Gastrointestinal Disorders
Nausea | 15 | 11
Constipation | 11 | 7
Vomiting | 11 | 6
Dyspepsia | 9 | 7
Dry Mouth | 5 | 4
Toothache | 4 | 3
Abdominal Discomfort | 3 | 2
Stomach Discomfort | 3 | 2
General Disorders and Administration Site Conditions
Fatigue | 6 | 4
Pain | 3 | 2
Musculoskeletal and Connective Tissue Disorders
Musculoskeletal Stiffness | 4 | 3
Pain in Extremity | 4 | 2
Myalgia | 2 | 1
Muscle Spasms | 2 | 1
Nervous System Disorders
Headache | 27 | 23
Dizziness | 10 | 7
Akathisia | 10 | 4
Sedation | 7 | 4
Extrapyramidal Disorder | 5 | 3
Tremor | 5 | 3
Somnolence | 5 | 3
Psychiatric Disorders
Agitation | 19 | 17
Insomnia | 18 | 13
Anxiety | 17 | 13
Restlessness | 5 | 3
Respiratory, Thoracic, and Mediastinal Disorders
Pharyngolaryngeal Pain | 3 | 2
Cough | 3 | 2

An examination of population subgroups did not reveal any clear evidence of differential adverse reaction incidence on the basis of age, gender, or race.

Adverse Reactions in Pediatric Patients (13 to 17 years) with Schizophrenia

The following findings are based on one 6-week, placebo-controlled trial in which oral aripiprazole was administered in doses ranging from 2 to 30 mg/day.

The incidence of discontinuation due to adverse reactions between aripiprazole-treated and placebo-treated pediatric patients (13 to 17 years) was 5% and 2%, respectively.

Commonly observed adverse reactions associated with the use of aripiprazole in pediatric patients 13 to 17 years with schizophrenia (incidence of 5% or greater and aripiprazole incidence at least twice that for placebo) were extrapyramidal disorder, somnolence, and tremor.

Adverse Reactions in Pediatric Patients (6 to 17 years) with Autistic Disorder

The following findings are based on two 8 week, placebo-controlled trials in which oral aripiprazole was administered in doses of 2 to 15 mg/day.

The incidence of discontinuation due to adverse reactions between aripiprazole-treated and placebo-treated pediatric patients (6 to 17 years) was 10% and 8%, respectively.

Commonly observed adverse reactions associated with the use of aripiprazole in pediatric patients (6 to 17 years) with autistic disorder (incidence of 5% or greater and aripiprazole incidence at least twice that for placebo) are shown in Table 14.

Table 14: Commonly Observed Adverse Reactions in Short-Term, Placebo-Controlled Trials of Pediatric Patients (6 to 17 years) with Autistic Disorder Treated with Oral Aripiprazole
 | Percentage of Patients Reporting Reaction
Preferred Term | Aripiprazole (n=212) | Placebo (n=101)
Sedation | 21 | 4
Fatigue | 17 | 2
Vomiting | 14 | 7
Somnolence | 10 | 4
Tremor | 10 | 0
Pyrexia | 9 | 1
Drooling | 9 | 0
Decreased Appetite | 7 | 2
Salivary Hypersecretion | 6 | 1
Extrapyramidal Disorder | 6 | 0
Lethargy | 5 | 0

Adverse Reactions in Pediatric Patients (6 to 18 years) with Tourette's Disorder

The following findings are based on one 8 week and one 10 week, placebo-controlled trials in which oral aripiprazole was administered in doses of 2 to 20 mg/day.

The incidence of discontinuation due to adverse reactions between aripiprazole-treated and placebo-treated pediatric patients (6 to 18 years) was 7% and 1%, respectively.

Commonly observed adverse reactions associated with the use of aripiprazole in pediatric patients (6 to 18 years) with Tourette's disorder (incidence of 5% or greater and aripiprazole incidence at least twice that for placebo) are shown in Table 15.

Table 15: Commonly Observed Adverse Reactions in Short-Term, Placebo-Controlled Trials of Pediatric Patients (6 to 18 years) with Tourette's Disorder Treated with Oral Aripiprazole
 | Percentage of Patients Reporting Reaction
Preferred Term | Aripiprazole (n=121) | Placebo (n=72)
Sedation | 13 | 6
Somnolence | 13 | 1
Nausea | 11 | 4
Headache | 10 | 3
Nasopharyngitis | 9 | 0
Fatigue | 8 | 0
Increased Appetite | 7 | 1

Table 16 enumerates the pooled incidence, rounded to the nearest percent, of adverse reactions that occurred during acute therapy (up to 6 weeks in schizophrenia, up to 4 weeks in another indication, up to 8 weeks in autistic disorder, and up to 10 weeks in Tourette's disorder), including only those reactions that occurred in 2% or more of pediatric patients treated with aripiprazole (doses ≥2 mg/day) and for which the incidence in patients treated with aripiprazole was greater than the incidence in patients treated with placebo.

Table 16: Adverse Reactions in Short-Term, Placebo-Controlled Trials of Pediatric Patients (6 to 18 years) Treated with Oral Aripiprazole
 | Percentage of Patients Reporting Reaction [Adverse reactions reported by at least 2% of pediatric patients treated with oral aripiprazole, except adverse reactions which had an incidence equal to or less than placebo.]
Preferred Term | Aripiprazole (n=732) | Placebo (n=370)
Eye Disorders
Blurred Vision | 3 | 0
Gastrointestinal Disorders
Abdominal Discomfort | 2 | 1
Vomiting | 8 | 7
Nausea | 8 | 4
Diarrhea | 4 | 3
Salivary Hypersecretion | 4 | 1
Abdominal Pain Upper | 3 | 2
Constipation | 2 | 2
General Disorders and Administration Site Conditions
Fatigue | 10 | 2
Pyrexia | 4 | 1
Irritability | 2 | 1
Asthenia | 2 | 1
Infections and Infestations
Nasopharyngitis | 6 | 3
Investigations
Weight Increased | 3 | 1
Metabolism and Nutrition Disorders
Increased Appetite | 7 | 3
Decreased Appetite | 5 | 4
Musculoskeletal and Connective Tissue Disorders
Musculoskeletal Stiffness | 2 | 1
Muscle Rigidity | 2 | 1
Nervous System Disorders
Somnolence | 16 | 4
Headache | 12 | 10
Sedation | 9 | 2
Tremor | 9 | 1
Extrapyramidal Disorder | 6 | 1
Akathisia | 6 | 4
Drooling | 3 | 0
Lethargy | 3 | 0
Dizziness | 3 | 2
Dystonia | 2 | 1
Respiratory, Thoracic, and Mediastinal Disorders
Epistaxis | 2 | 1
Skin and Subcutaneous Tissue Disorders
Rash | 2 | 1

Adverse Reactions in Adult Patients Receiving Aripiprazole as Adjunctive Treatment of Major Depressive Disorder

The following findings are based on a pool of two placebo-controlled trials of patients with major depressive disorder in which aripiprazole was administered at doses of 2 to 20 mg as adjunctive treatment to continued antidepressant therapy.

The incidence of discontinuation due to adverse reactions was 6% for adjunctive aripiprazole-treated patients and 2% for adjunctive placebo-treated patients.

The commonly observed adverse reactions associated with the use of adjunctive aripiprazole in patients with major depressive disorder (incidence of 5% or greater and aripiprazole incidence at least twice that for placebo) were: akathisia, restlessness, insomnia, constipation, fatigue, and blurred vision.

Table 17 enumerates the pooled incidence, rounded to the nearest percent, of adverse reactions that occurred during acute therapy (up to 6 weeks), including only those adverse reactions that occurred in 2% or more of patients treated with adjunctive aripiprazole (doses ≥2 mg/day) and for which the incidence in patients treated with adjunctive aripiprazole was greater than the incidence in patients treated with adjunctive placebo in the combined dataset.

Table 17: Adverse Reactions in Short-Term, Placebo-Controlled Adjunctive Trials in Patients with Major Depressive Disorder
 | Percentage of Patients Reporting Reaction [Adverse reactions reported by at least 2% of patients treated with adjunctive Aripiprazole, except adverse reactions which had an incidence equal to or less than placebo.]
Preferred Term | Aripiprazole + ADT [Antidepressant Therapy] (n=371) | Placebo + ADT (n=366)
Eye Disorders
Blurred Vision | 6 | 1
Gastrointestinal Disorders
Constipation | 5 | 2
General Disorders and Administration Site Conditions
Fatigue | 8 | 4
Feeling Jittery | 3 | 1
Infections and Infestations
Upper Respiratory Tract Infection | 6 | 4
Investigations
Weight Increased | 3 | 2
Metabolism and Nutrition Disorders
Increased Appetite | 3 | 2
Musculoskeletal and Connective Tissue Disorders
Arthralgia | 4 | 3
Myalgia | 3 | 1
Nervous System Disorders
Akathisia | 25 | 4
Somnolence | 6 | 4
Tremor | 5 | 4
Sedation | 4 | 2
Dizziness | 4 | 2
Disturbance in Attention | 3 | 1
Extrapyramidal Disorder | 2 | 0
Psychiatric Disorders
Restlessness | 12 | 2
Insomnia | 8 | 2

Dose-Related Adverse Reactions

Schizophrenia

Dose response relationships for the incidence of adverse reactions were evaluated from four trials in adult patients with schizophrenia comparing various fixed doses (2, 5, 10, 15, 20, and 30 mg/day) of oral aripiprazole to placebo. This analysis, stratified by study, indicated that the adverse reaction to have a possible dose response relationship, and then most prominent only with 30 mg, was somnolence [including sedation]; (incidences were placebo, 7.1%; 10 mg, 8.5%; 15 mg, 8.7%; 20 mg, 7.5%; 30 mg, 12.6%).

In the study of pediatric patients (13 to 17 years of age) with schizophrenia, three common adverse reactions appeared to have a possible dose response relationship: extrapyramidal disorder (incidences were placebo, 5.0%; 10 mg, 13.0%; 30 mg, 21.6%); somnolence (incidences were placebo, 6.0%; 10 mg, 11.0%; 30 mg, 21.6%); and tremor (incidences were placebo, 2.0%; 10 mg, 2.0%; 30 mg, 11.8%).

Autistic Disorder

In a study of pediatric patients (6 to 17 years of age) with autistic disorder, one common adverse reaction had a possible dose response relationship: fatigue (incidences were placebo, 0%; 5 mg, 3.8%; 10 mg, 22.0%; 15 mg, 18.5%).

Tourette's Disorder

In a study of pediatric patients (7 to 17 years of age) with Tourette's disorder, no common adverse reaction(s) had a dose response relationship.

Extrapyramidal Symptoms

Schizophrenia

In short-term, placebo-controlled trials in schizophrenia in adults, the incidence of reported EPS-related events, excluding events related to akathisia, for aripiprazole-treated patients was 13% vs. 12% for placebo; and the incidence of akathisiarelated events for aripiprazole-treated patients was 8% vs. 4% for placebo. In the short-term, placebo-controlled trial of schizophrenia in pediatric patients (13 to 17 years), the incidence of reported EPS-related events, excluding events related to akathisia, for aripiprazole-treated patients was 25% vs. 7% for placebo; and the incidence of akathisia-related events for aripiprazole-treated patients was 9% vs. 6% for placebo.

Objectively collected data from those trials was collected on the Simpson Angus Rating Scale (for EPS), the Barnes Akathisia Scale (for akathisia), and the Assessments of Involuntary Movement Scales (for dyskinesias). In the adult schizophrenia trials, the objectively collected data did not show a difference between aripiprazole and placebo, with the exception of the Barnes Akathisia Scale (aripiprazole, 0.08; placebo, –0.05). In the pediatric (13 to 17 years) schizophrenia trial, the objectively collected data did not show a difference between aripiprazole and placebo, with the exception of the Simpson Angus Rating Scale (aripiprazole, 0.24; placebo, –0.29).

Similarly, in a long-term (26 week), placebo-controlled trial of schizophrenia in adults, objectively collected data on the Simpson Angus Rating Scale (for EPS), the Barnes Akathisia Scale (for akathisia), and the Assessments of Involuntary Movement Scales (for dyskinesias) did not show a difference between aripiprazole and placebo.

Major Depressive Disorder

In the short-term, placebo-controlled trials in major depressive disorder, the incidence of reported EPS-related events, excluding events related to akathisia, for adjunctive aripiprazole- treated patients was 8% vs. 5% for adjunctive placebotreated patients; and the incidence of akathisia-related events for adjunctive aripiprazole-treated patients was 25% vs. 4% for adjunctive placebo-treated patients.

In the major depressive disorder trials, the Simpson Angus Rating Scale and the Barnes Akathisia Scale showed a significant difference between adjunctive aripiprazole and adjunctive placebo (aripiprazole, 0.31; placebo, 0.03 and aripiprazole, 0.22; placebo, 0.02). Changes in the Assessments of Involuntary Movement Scales were similar for the adjunctive aripiprazole and adjunctive placebo groups.

Autistic Disorder

In the short-term, placebo-controlled trials in autistic disorder in pediatric patients (6 to 17 years), the incidence of reported EPS-related events, excluding events related to akathisia, for aripiprazole-treated patients was 18% vs. 2% for placebo and the incidence of akathisia-related events for aripiprazole-treated patients was 3% vs. 9% for placebo.

In the pediatric (6 to 17 years) short-term autistic disorder trials, the Simpson Angus Rating Scale showed a significant difference between aripiprazole and placebo (aripiprazole, 0.1; placebo, – 0.4). Changes in the Barnes Akathisia Scale and the Assessments of Involuntary Movement Scales were similar for the aripiprazole and placebo groups.

Tourette's Disorder

In the short-term, placebo-controlled trials in Tourette's disorder in pediatric patients (6 to 18 years), the incidence of reported EPS-related events, excluding events related to akathisia, for aripiprazole-treated patients was 7% vs. 6% for placebo and the incidence of akathisia-related events for aripiprazole-treated patients was 4% vs. 6% for placebo.

In the pediatric (6 to 18 years) short-term Tourette's disorder trials, changes in the Simpson Angus Rating Scale, Barnes Akathisia Scale and Assessments of Involuntary Movement Scale were not clinically meaningfully different for aripiprazole and placebo.

Dystonia

Symptoms of dystonia, prolonged abnormal contractions of muscle groups, may occur in susceptible individuals during the first few days of treatment. Dystonic symptoms include spasm of the neck muscles, sometimes progressing to tightness of the throat, swallowing difficulty, difficulty breathing, and/or protrusion of the tongue. While these symptoms can occur at low doses, they occur more frequently and with greater severity with high potency and at higher doses of first generation antipsychotic drugs. An elevated risk of acute dystonia is observed in males and younger age groups.

Additional Findings Observed in Clinical Trials

Adverse Reactions in Long-Term, Double-Blind, Placebo-Controlled Trials

The adverse reactions reported in a 26-week, double-blind trial comparing oral aripiprazole and placebo in patients with schizophrenia were generally consistent with those reported in the short-term, placebo-controlled trials, except for a higher incidence of tremor [8% (12/153) for aripiprazole tablets vs. 2% (3/153) for placebo]. In this study, the majority of the cases of tremor were of mild intensity (8/12 mild and 4/12 moderate), occurred early in therapy (9/12 ≤49 days), and were of limited duration (7/12 ≤10 days). Tremor led to discontinuation (<1%) of aripiprazole. In addition, in a long-term (52 weeks), active-controlled study, the incidence of tremor was 5% (40/859) for aripiprazole.

Other Adverse Reactions Observed During Clinical Trial Evaluation of Aripiprazole

Other adverse reactions associated with aripiprazole are presented below. The following listing does not include reactions: 1) already listed in previous tables or elsewhere in labeling, 2) for which a drug cause was remote, 3) which were so general as to be uninformative, 4) which were not considered to have significant clinical implications, or 5) which occurred at a rate equal to or less than placebo.

Reactions are categorized by body system according to the following definitions: frequent adverse reactions are those occurring in at least 1/100 patients; infrequent adverse reactions are those occurring in 1/100 to 1/1,000 patients; rare reactions are those occurring in fewer than 1/1,000 patients:

Adults - Oral Administration

- Blood and Lymphatic System Disorders: rare - thrombocytopenia
- Cardiac Disorders: infrequent – bradycardia, palpitations, rare – atrial flutter, cardio-respiratory arrest, atrioventricular block, atrial fibrillation, angina pectoris, myocardial ischemia, myocardial infarction, cardiopulmonary failure
- Eye Disorders: infrequent – photophobia; rare - diplopia
- Gastrointestinal Disorders: infrequent - gastroesophageal reflux disease
- General Disorders and Administration Site Conditions: frequent - asthenia; infrequent – peripheral edema, chest pain; rare – face edema
- Hepatobiliary Disorders: rare - hepatitis, jaundice
- Immune System Disorders: rare - hypersensitivity
- Injury, Poisoning, and Procedural Complications: infrequent - fall; rare-heat stroke
- Investigations: frequent - blood prolactin decreased, weight decreased, infrequent - hepatic enzyme increased, blood glucose increased, blood lactate dehydrogenase increased, gamma glutamyl transferase increased; rare - blood prolactin increased, blood urea increased, blood creatinine increased, blood bilirubin increased, electrocardiogram QT prolonged, glycosylated hemoglobin increased
- Metabolism and Nutrition Disorders: frequent – anorexia; rare - hypokalemia, hyponatremia, hypoglycemia
- Musculoskeletal and Connective Tissue Disorders: infrequent - muscular weakness, muscle tightness; rare – rhabdomyolysis, mobility decreased
- Nervous System Disorders: infrequent - parkinsonism, memory impairment, cogwheel rigidity, hypokinesia, bradykinesia; rare – akinesia, myoclonus, coordination abnormal, speech disorder, Grand Mal convulsion; <1/10,000 patients - choreoathetosis
- Psychiatric Disorders: infrequent – aggression, loss of libido, delirium; rare - libido increased, anorgasmia, tic, homicidal ideation, catatonia, sleep walking
- Renal and Urinary Disorders: rare - urinary retention, nocturia
- Reproductive System and Breast Disorders: infrequent - erectile dysfunction; rare - gynaecomastia, menstruation irregular, amenorrhea, breast pain, priapism
- Respiratory, Thoracic, and Mediastinal Disorders: infrequent - nasal congestion, dyspnea
- Skin and Subcutaneous Tissue Disorders: infrequent - rash, hyperhidrosis, pruritus, photosensitivity reaction, alopecia; rare - urticaria
- Vascular Disorders: infrequent – hypotension, hypertension

Pediatric Patients - Oral Administration

Most adverse reactions observed in the pooled database of 1,686 pediatric patients, aged 6 to 18 years, were also observed in the adult population. Additional adverse reactions observed in the pediatric population are listed below.

- Eye Disorders: infrequent - oculogyric crisis
- Gastrointestinal Disorders: infrequent -tongue dry, tongue spasm
- Investigations: frequent - blood insulin increased
- Nervous System Disorders: infrequent - sleep talking
- Renal and Urinary Disorders: frequent - enuresis
- Skin and Subcutaneous Tissue Disorders: infrequent- hirsutism

6.2 Postmarketing Experience

The following adverse reactions have been identified during post-approval use of aripiprazole. Because these reactions are reported voluntarily from a population of uncertain size, it is not always possible to reliably estimate their frequency or establish a causal relationship to drug exposure: occurrences of allergic reaction (anaphylactic reaction, angioedema, laryngospasm, pruritus/urticaria, or oropharyngeal spasm), blood glucose fluctuation, Drug Reaction with Eosinophilia and Systemic Symptoms (DRESS), hiccups, oculogyric crisis, and pathological gambling.

7 DRUG INTERACTIONS

7.1 Drugs Having Clinically Important Interactions with OPIPZA

Table 18 includes clinically important drug interactions with OPIPZA.

Table 18: Clinically Important Drug Interactions with OPIPZA
Strong CYP3A4 Inhibitors AND/OR Strong CYP2D6 Inhibitors
Clinical Rationale | Concomitant use of aripiprazole with strong CYP3A4 and/or CYP2D6 inhibitors increased the exposure of aripiprazole [see Clinical Pharmacology (12.3)].
Clinical Recommendation | Reduce the dosage of OPIPZA when administered concomitantly with a strong CYP3A4 inhibitor and/or strong CYP2D6 inhibitor [see Dosage and Administration (2.6)].
Strong CYP3A4 Inducers
Clinical Rationale | Concomitant use of aripiprazole and carbamazepine decreased the exposure of aripiprazole [see Clinical Pharmacology (12.3)].
Clinical Recommendation | Consider increasing the dosage of OPIPZA when administered concomitantly with a strong CYP3A4 inducer [see Dosage and Administration (2.6)].
Antihypertensive Drugs
Clinical Rationale | Due to its alpha-adrenergic antagonism, aripiprazole has the potential to enhance the effect of certain antihypertensive agents.
Clinical Recommendation | Monitor blood pressure and adjust dose accordingly [see Warnings and Precautions (5.8)].
Benzodiazepines
Clinical Rationale | The intensity of sedation was greater with the combination of oral aripiprazole and lorazepam as compared to that observed with aripiprazole alone. The orthostatic hypotension observed was greater with the combination as compared to that observed with lorazepam alone [see Warnings and Precautions (5.8)].
Clinical Recommendation | Monitor sedation and blood pressure. Adjust dose accordingly.

7.2 Drugs Having No Clinically Important Interactions with OPIPZA

Based on pharmacokinetic studies, no dosage adjustment of aripiprazole is required when administered concomitantly with famotidine, valproate, lithium, lorazepam.

In addition, no dosage adjustment is necessary for substrates of CYP2D6, CYP2C9, CYP2C19, or CYP3A4 when coadministered with OPIPZA. Additionally, no dosage adjustment is necessary for valproate, lithium, lamotrigine, lorazepam, or sertraline when co-administered with OPIPZA [see Clinical Pharmacology (12.3)].

8 USE IN SPECIFIC POPULATIONS

8.1 Pregnancy

Pregnancy Exposure Registry

There is a pregnancy exposure registry that monitors pregnancy outcomes in women exposed to atypical antipsychotics, including aripiprazole, during pregnancy. Healthcare providers are encouraged to advise patients to register by contacting the National Pregnancy Registry for Atypical Antipsychotics at 1-866-961-2388 or visiting online at http://womensmentalhealth.org/clinical-and-research-programs/pregnancyregistry/.

Risk Summary

Neonates exposed to antipsychotic drugs, including OPIPZA, during the third trimester of pregnancy are at risk for extrapyramidal and/or withdrawal symptoms following delivery (see Clinical Considerations). Overall available data from published epidemiologic studies of pregnant women exposed to aripiprazole have not established a drug-associated risk of major birth defects, miscarriage, or adverse maternal or fetal outcomes (see Data). There are risks to the mother associated with untreated schizophrenia, or major depressive disorder, and with exposure to antipsychotics, including OPIPZA during pregnancy (see Clinical Considerations).

In animal reproduction studies, oral and intravenous aripiprazole administration during organogenesis in rats and/or rabbits at doses 10 and 19 times, respectively, the maximum recommended human dose (MRHD) of 30 mg/day based on mg/m^2 body surface area, produced fetal death, decreased fetal weight, undescended testicles, delayed skeletal ossification, skeletal abnormalities, and diaphragmatic hernia. Oral and intravenous aripiprazole administration during the pre- and post-natal period in rats at doses 10 times the MRHD based on mg/m^2 body surface area, produced prolonged gestation, stillbirths, decreased pup weight, and decreased pup survival (see Data).

The background risk of major birth defects and miscarriage for the indicated population is unknown. All pregnancies have a background risk of birth defect, loss, or other adverse outcomes. In the U.S. general population, the estimated background risk of major birth defects and miscarriage in clinically recognized pregnancies is 2 % to 4% and 15% to 20%, respectively.

Clinical Considerations

Disease-associated maternal and/or embryo/fetal risk

There is a risk to the mother from untreated schizophrenia, including increased risk of relapse, hospitalization, and suicide. Schizophrenia is associated with increased adverse perinatal outcomes, including preterm birth. It is not known if this is a direct result of the illness or other comorbid factors.

A prospective, longitudinal study followed 201 pregnant women with a history of major depressive disorder who were euthymic and taking antidepressants at the beginning of pregnancy. The women who discontinued antidepressants during pregnancy were more likely to experience a relapse of major depression than women who continued antidepressants. Consider the risk of untreated depression when discontinuing or changing treatment with antidepressant medication during pregnancy and postpartum.

Fetal/Neonatal Adverse Reactions

Extrapyramidal and/or withdrawal symptoms, including agitation, hypertonia, hypotonia, tremor, somnolence, respiratory distress, and feeding disorder have been reported in neonates who were exposed to antipsychotic drugs (including aripiprazole) during the third trimester of pregnancy. These symptoms have varied in severity. Monitor neonates for extrapyramidal and/or withdrawal symptoms and manage symptoms appropriately. Some neonates recovered within hours or days without specific treatment; others required prolonged hospitalization.

Data

Human Data

Published data from observational studies, birth registries, and case reports on the use of atypical antipsychotics during pregnancy do not report a clear association with antipsychotics and major birth defects. A retrospective study from a Medicaid database of 9,258 women exposed to antipsychotics during pregnancy did not indicate an overall increased risk for major birth defects.

Animal Data

In animal studies, aripiprazole demonstrated developmental toxicity, including possible teratogenic effects in rats and rabbits.

In pregnant rats treated orally with aripiprazole during organogenesis at doses of 3, 10, and 30 mg/kg/day, which are approximately 1, 3 and 10 times the MRHD of 30 mg/day based on mg/m^2 body surface area, a slight prolongation of gestation and delay in fetal development, as evidenced by decreased fetal weight and undescended testes, were observed at 10 times the MRHD. Delayed skeletal ossification was observed at 3 and 10 times the MRHD. Delivered offspring had increased incidences of hepatodiaphragmatic nodules and diaphragmatic hernia were observed at 10 times the MRHD (the other dose groups were not examined for these findings). Postnatally, delayed vaginal opening was seen at 3 and 10 times the MRHD. Impaired reproductive performance (decreased fertility rate, corpora lutea, implants, live fetuses, and increased post-implantation loss, likely mediated through effects on female offspring) were observed at 10 times the MRHD; however, there was no evidence to suggest that these developmental effects were secondary to maternal toxicity.

In pregnant rabbits treated orally with aripiprazole during organogenesis at doses of 10, 30, and 100 mg/kg/day which are 6, 19, and 65 times the MRHD of 30 mg/day based on mg/m^2 body surface area, decreased maternal food consumption, and increased abortions as well as increased fetal mortality were observed at 65 times the MRHD. Decreased fetal weight and increased incidence of fused sternebrae were observed at 19 and 65 times the MRHD.

In rats treated orally with aripiprazole peri- and postnatally from gestation Day 17 through postpartum Day 21 at doses of 3, 10, and 30 mg/kg/day which are 1, 3, and 10 times the MRHD of 30 mg/day based on mg/m ^2 body surface area slight maternal toxicity and slightly prolonged gestation were observed at 10 times the MRHD. An increase in stillbirths and, decreases in pup weight (persisting into adulthood) and survival were also seen at this dose.

8.2 Lactation

Risk Summary

Limited data from published literature report the presence of aripiprazole in human breast milk, at relative infant doses ranging between 0.7% to 8.3% of the maternal weight-adjusted dosage. There are reports of poor weight gain in breastfed infants exposed to aripiprazole and reports of inadequate milk supply in lactating women taking aripiprazole.

The development and health benefits of breastfeeding should be considered along with the mother's clinical need for OPIPZA and any potential adverse effects on the breastfed infant from OPIPZA or from the underlying maternal condition.

8.4 Pediatric Use

Safety and effectiveness of OPIPZA in pediatric patients with major depressive disorder have not been established.

The pharmacokinetics of aripiprazole and dehydro-aripiprazole in pediatric patients 10 to 17 years of age were similar to those in adults after correcting for the differences in body weight [see Clinical Pharmacology (12.3)].

Schizophrenia

Safety and effectiveness in pediatric patients with schizophrenia were established in a 6-week, placebo-controlled clinical trial of another oral aripiprazole product in 202 pediatric patients aged 13 to 17 years [see Clinical Studies (14.2)]. Although maintenance efficacy in pediatric patients has not been systematically evaluated, maintenance efficacy can be extrapolated from adult data along with comparisons of aripiprazole pharmacokinetic parameters in adult and pediatric patients.

Irritability Associated with Autistic Disorder

Safety and effectiveness in pediatric patients demonstrating irritability associated with autistic disorder were established in two 8 week, placebo-controlled clinical trials of another oral aripiprazole product in 212 pediatric patients aged 6 to 17 years [Clinical Studies (14.4)]. A maintenance trial was conducted in pediatric patients (6 to 17 years of age) with irritability associated with autistic disorder. The first phase of this trial was an open-label, flexibly dosed (aripiprazole 2 to 15 mg/day) phase in which patients were stabilized (defined as > 25% improvement on the ABC-I subscale, and a CGI-I rating of "much improved" or "very much improved") on aripiprazole for 12 consecutive weeks. Overall, 85 patients were stabilized and entered the second, 16 week, double-blind phase where they were randomized to either continue aripiprazole treatment or switch to placebo. In this trial, the efficacy of aripiprazole for the maintenance treatment of irritability associated with autistic disorder was not established.

Tourette's Disorder

Safety and effectiveness of aripiprazole in pediatric patients with Tourette's Disorder were established in one 8 week (aged 7 to 17 years) and one 10-week trial (aged 6 to 18 years) of another oral aripiprazole product in 194 pediatric patients [see Clinical Studies (14.5)]. Maintenance efficacy in pediatric patients has not been systematically evaluated.

Juvenile Animal Studies

Aripiprazole in juvenile rats caused mortality, CNS clinical signs, impaired memory and learning, and delayed sexual maturation when administered at oral doses of 10, 20, 40 mg/kg/day from weaning (21 days old) through maturity (80 days old). At 40 mg/kg/day, mortality, decreased activity, splayed hind limbs, hunched posture, ataxia, tremors and other CNS signs were observed in both genders. In addition, delayed sexual maturation was observed in males. At all doses and in a dose-dependent manner, impaired memory and learning, increased motor activity, and histopathology changes in the pituitary (atrophy), adrenals (adrenocortical hypertrophy), mammary glands (hyperplasia and increased secretion), and female reproductive organs (vaginal mucification, endometrial atrophy, decrease in ovarian corpora lutea) were observed. The changes in female reproductive organs were considered secondary to the increase in prolactin serum levels. A No Observed Adverse Effect Level (NOAEL) could not be determined and, at the lowest tested dose of 10 mg/kg/day, there is no safety margin relative to the systemic exposures (AUC0-24) for aripiprazole or its major active metabolite in adolescents at the maximum recommended pediatric dose of 15 mg/day. All drug-related effects were reversible after a 2 month recovery period, and most of the drug effects in juvenile rats were also observed in adult rats from previously conducted studies.

Aripiprazole in juvenile dogs (2 months old) caused CNS clinical signs of tremors, hypoactivity, ataxia, recumbency and limited use of hind limbs when administered orally for 6 months at 3, 10, 30 mg/kg/day. Mean body weight and weight gain were decreased up to 18% in females in all drug groups relative to control values. A NOAEL could not be determined and, at the lowest tested dose of 3 mg/kg/day, there is no safety margin relative to the systemic exposures (AUC0-24) for aripiprazole or its major active metabolite in adolescents at the maximum recommended pediatric dose of 15 mg/day. All drug-related effects were reversible after a 2 month recovery period.

8.5 Geriatric Use

No dosage adjustment of OPIPZA is recommended for geriatric patients [see Clinical Pharmacology (12.3)].

Of the 13,543 patients treated with oral aripiprazole in clinical trials, 1,073 (8%) were ≥65 years old and 799 (6%) were ≥75 years old. Placebo-controlled studies of oral aripiprazole in schizophrenia, major depressive disorder, or another indication did not include sufficient numbers of patients aged 65 and over to determine whether they respond differently from younger patients.

Elderly patients with dementia-related psychosis treated with antipsychotic drugs are at an increased risk of death. OPIPZA is not approved for the treatment of patients with dementia-related psychosis [see Boxed Warning and Warnings and Precautions (5.1)].

8.6 CYP2D6 Poor Metabolizers

OPIPZA dosage adjustment is recommended in known CYP2D6 poor metabolizers due to high aripiprazole concentrations. Approximately 8% of Caucasians and 3% to 8% of Black/African Americans cannot metabolize CYP2D6 substrates and are classified as poor metabolizers (PM) [see Dosage and Administration (2.6) and Clinical Pharmacology (12.3)].

8.7 Renal Impairment

No dosage adjustment for OPIPZA is required on the basis of a patient's renal function (glomerular filtration rate between 15 and 90 mL/minute) [see Clinical Pharmacology (12.3)].

8.8 Hepatic Impairment

No dosage adjustment for OPIPZA is required on the basis of a patient's hepatic function (Child-Pugh scores between 5 and 15) [see Clinical Pharmacology (12.3)].

9 DRUG ABUSE AND DEPENDENCE

9.1 Controlled Substance

OPIPZA contains aripiprazole, which is not a controlled substance.

9.2 Abuse

Aripiprazole has not been systematically studied in humans for its potential for abuse, tolerance, or physical dependence. Consequently, patients should be evaluated carefully for a history of drug abuse, and such patients should be observed closely for signs of aripiprazole misuse or abuse (e.g., development of tolerance, increases in dose, drug-seeking behavior).

9.3 Dependence

In physical dependence studies in monkeys, withdrawal symptoms were observed upon abrupt cessation of dosing. While the clinical trials did not reveal any tendency for any drug-seeking behavior, these observations were not systematic and it is not possible to predict on the basis of this limited experience the extent to which a CNS-active drug will be misused, diverted, and/or abused once marketed.

10 OVERDOSAGE

Human Experience

In clinical trials and in postmarketing experience, adverse reactions of deliberate or accidental overdosage with oral aripiprazole have been reported worldwide. These include overdoses with oral aripiprazole alone and in combination with other substances. No fatality was reported with aripiprazole alone. The largest known dose with a known outcome involved acute ingestion of 1,260 mg of oral aripiprazole (42 times the maximum recommended daily dose) by a patient who fully recovered. Deliberate or accidental overdosage was also reported in patients age 12 years and younger involving oral aripiprazole ingestions up to 195 mg (6.5 times the maximum recommended daily dose) with no fatalities.

Common adverse reactions (reported in at least 5% of all overdose cases) reported with oral aripiprazole overdosage (alone or in combination with other substances) include vomiting, somnolence, and tremor. Other clinically important signs and symptoms observed in one or more patients with aripiprazole overdoses (alone or with other substances) include acidosis, aggression, aspartate aminotransferase increased, atrial fibrillation, bradycardia, coma, confusional state, convulsion, blood creatine phosphokinase increased, depressed level of consciousness, hypertension, hypokalemia, hypotension, lethargy, loss of consciousness, QRS complex prolonged, QT prolonged, pneumonia aspiration, respiratory arrest, status epilepticus, and tachycardia.

Management of Overdosage

Consider contacting the Poison Help line (1-800-222-1222) or medical toxicologist for additional overdosage management recommendations.

No specific information is available on the treatment of overdose with OPIPZA. An electrocardiogram should be obtained in case of overdosage and if QT interval prolongation is present, cardiac monitoring should be instituted. Otherwise, management of overdose should concentrate on supportive therapy, maintaining an adequate airway, oxygenation and ventilation, and management of symptoms. Close medical supervision and monitoring should continue until the patient recovers.

Charcoal: In the event of an overdose of OPIPZA, an early charcoal administration may be useful in partially preventing the absorption of aripiprazole. Administration of 50 g of activated charcoal, one hour after a single 15 mg oral dose of aripiprazole, decreased the mean AUC and Cmax of aripiprazole by 50%.

Hemodialysis: Although there is no information on the effect of hemodialysis in treating an overdose with OPIPZA, hemodialysis is unlikely to be useful in overdose management since aripiprazole is highly bound to plasma proteins.

11 DESCRIPTION

OPIPZA contains aripiprazole, an atypical antipsychotic drug. Aripiprazole is 7-[4-[4-(2,3-dichlorophenyl)-1-piperazinyl]butoxy]-3,4-dihydrocarbostyril. Aripiprazole has a pKa of 6.2. It is freely soluble in dichloromethane, sparingly soluble in toluene, and insoluble in methanol and water. The empirical formula is C23H27Cl2N3O2 with a molecular weight of 448.38. The chemical structure is:

OPIPZA is for oral administration and is available in 2 mg, 5 mg, and 10 mg strengths. Inactive ingredients include hydroxypropyl cellulose, sodium lauryl sulfate, and sucralose. Imprinting ink contains glycerin, FD&C Blue No.1, polysorbate 20, and propylene glycol.

12 CLINICAL PHARMACOLOGY

12.1 Mechanism of Action

The mechanism of action of aripiprazole in the listed indications, is unclear. However, the efficacy of aripiprazole in the listed indications could be mediated through a combination of partial agonist activity at D2 and 5-HT1A receptors and antagonist activity at 5-HT2A receptors.

12.2 Pharmacodynamics

Aripiprazole exhibits high affinity for dopamine D2 and D3, serotonin 5-HT1A and 5-HT2A receptors (Ki values of 0.34 nM, 0.8 nM, 1.7 nM, and 3.4 nM, respectively), moderate affinity for dopamine D4, serotonin 5-HT2C and 5-HT7, alpha1-adrenergic and histamine H1 receptors (Ki values of 44 nM, 15 nM, 39 nM, 57 nM, and 61 nM, respectively), and moderate affinity for the serotonin reuptake site (Ki=98 nM). Aripiprazole has no appreciable affinity for cholinergic muscarinic receptors (IC50>1000 nM).

12.3 Pharmacokinetics

Aripiprazole oral film activity is presumably primarily due to the parent drug, aripiprazole, and to a lesser extent, to its major metabolite, dehydro-aripiprazole, which has been shown to have affinities for D2 receptors similar to the parent drug and represents 40% of the parent drug exposure in plasma.

Absorption

Following administration of aripiprazole oral film, the median (range) time to reach peak plasma concentrations (Tmax) occurs at of 1.5 (1, 6) hours. In two studies comparing the pharmacokinetics of 10 mg aripiprazole oral film to 10 mg aripiprazole tablets under fasting and fed conditions in healthy subjects, the oral film to tablet ratios of geometric mean Cmax and AUC values under fasting conditions were 114% and 106%, respectively, the oral film to tablet ratios of geometric mean Cmax and AUC values under fed conditions were 91% and 95%, respectively.

Steady-state concentrations are attained within 14 days of dosing for both active moieties. Aripiprazole accumulation is predictable from single-dose pharmacokinetics. At steady-state, the pharmacokinetics of aripiprazole is dose-proportional.

Effect of Food

OPIPZA can be administered with or without food. Administration of a 10 mg aripiprazole oral film with a standard highfat (800 – 1,000 Kcal) meal did not significantly affect the Cmax or AUC of aripiprazole, but increased median (range) Tmax for aripiprazole from 1.5 (1, 6) to 6 (1.5, 12) hours.

Distribution

The steady-state volume of distribution of aripiprazole following intravenous administration is high (404 L or 4.9 L/kg), indicating extensive extravascular distribution. At therapeutic concentrations, aripiprazole and its major metabolite are greater than 99% bound to serum proteins, primarily to albumin. In healthy human volunteers administered 0.5 to 30 mg/day aripiprazole for 14 days, there was dose-dependent D2 receptor occupancy indicating brain penetration of aripiprazole in humans.

Elimination

The mean elimination half-lives are about 75 hours and 94 hours for aripiprazole and dehydro-aripiprazole, respectively. For CYP2D6 poor metabolizers, the mean elimination half-life for aripiprazole is about 146 hours.

Metabolism

Elimination of aripiprazole is mainly through hepatic metabolism involving two P450 isozymes, CYP2D6 and CYP3A4.

Aripiprazole is metabolized primarily by three biotransformation pathways: dehydrogenation, hydroxylation, and Ndealkylation. Based on in vitro studies, CYP3A4 and CYP2D6 enzymes are responsible for dehydrogenation and hydroxylation of aripiprazole, and N-dealkylation is catalyzed by CYP3A4. Aripiprazole is the predominant drug moiety in the systemic circulation. At steady-state, dehydro-aripiprazole, the active metabolite, represents about 40% of aripiprazole AUC in plasma.

Excretion

Following a single oral dose of [^14C]-labeled aripiprazole, approximately 25% and 55% of the administered radioactivity was recovered in the urine and feces, respectively. Less than 1% of unchanged aripiprazole was excreted in the urine and approximately 18% of the oral dose was recovered unchanged in the feces.

Drug Interaction Studies

Effect of other drugs on the exposures of aripiprazole and dehydro-aripiprazole are summarized in Figure 1 and Figure 2, respectively. Based on simulation, a 4.5-fold increase in mean Cmax and AUC values at steady-state is expected when extensive metabolizers of CYP2D6 are administered with both strong CYP2D6 and CYP3A4 inhibitors. A 3-fold increase in mean Cmax and AUC values at steady-state is expected in poor metabolizers of CYP2D6 administered with strong CYP3A4 inhibitors.

Figure 1: The Effect of Other Drugs on Aripiprazole Tablet Pharmacokinetics

Figure 2: The Effect of Other Drugs on Dehydro-Aripiprazole Pharmacokinetics

The effect of aripiprazole on the exposures of other drugs are summarized in Figure 3. A population PK analysis in patients with major depressive disorder showed no substantial change in plasma concentrations of fluoxetine (20 or 40 mg/day), paroxetine CR (37.5 or 50 mg/day), or sertraline (100 or 150 mg/day) dosed to steady-state. The steady-state plasma concentrations of fluoxetine and norfluoxetine increased by about 18% and 36%, respectively, and concentrations of paroxetine decreased by about 27%. The steady-state plasma concentrations of sertraline and desmethylsertraline were not substantially changed when these antidepressant therapies were co-administered with aripiprazole.

Figure 3: The Effect of Aripiprazole on Pharmacokinetics of Other Drugs

Specific Populations

Exposure of aripiprazole and dehydro-aripiprazole in specific populations is summarized in Figure 4 and Figure 5, respectively. In addition, in pediatric patients (10 to 17 years of age) administered with aripiprazole (20 mg to 30 mg), the body weight corrected aripiprazole clearance was similar to the adults.

Figure 4: Effect of Intrinsic Factors on Aripiprazole Pharmacokinetics

Figure 5: Effect of Intrinsic Factors on Dehydro-Aripiprazole Pharmacokinetics

13 NONCLINICAL TOXICOLOGY

13.1 Carcinogenesis, Mutagenesis, Impairment of Fertility

Carcinogenesis

Lifetime carcinogenicity studies were conducted in ICR mice, F344 rats, and Sprague-Dawley (SD) rats. Aripiprazole was administered for 2 years in the diet at doses of 1, 3, 10, and 30 mg/kg/day to ICR mice and 1, 3, and 10 mg/kg/day to F344 rats (0.2, 0.5, 2 and 5 times and 0.3, 1 and 3 times the MRHD of 30 mg/day based on mg/m^2 body surface area, respectively). In addition, SD rats were dosed orally for 2 years at 10, 20, 40, and 60 mg/kg/day, which are 3, 6, 13 and 19 times the MRHD based on mg/m^2 body surface area. Aripiprazole did not induce tumors in male mice or male rats. In female mice, the incidences of pituitary gland adenomas and mammary gland adenocarcinomas and adenoacanthomas were increased at dietary doses of 3 to 30 mg/kg/day (0.5 to 5 times the MRHD). In female rats, the incidence of mammary gland fibroadenomas was increased at a dietary dose of 10 mg/kg/day (3 times the MRHD); and the incidences of adrenocortical carcinomas and combined adrenocortical adenomas/carcinomas were increased at an oral dose of 60 mg/kg/day (19 times the MRHD).

An increase in mammary, pituitary, and endocrine pancreas neoplasms has been found in rodents after chronic administration of other antipsychotic drugs and is considered to be mediated by prolonged dopamine D2-receptor antagonism and hyperprolactinemia. Serum prolactin was not measured in the aripiprazole carcinogenicity studies. However, increases in serum prolactin levels were observed in female mice in a 13 week dietary study at the doses associated with mammary gland and pituitary tumors. Serum prolactin was not increased in female rats in 4 week and 13 week dietary studies at the dose associated with mammary gland tumors. The relevance for human risk of the findings of prolactin-mediated endocrine tumors in rodents is unclear.

Mutagenesis

The mutagenic potential of aripiprazole was tested in the in vitro bacterial reverse-mutation assay, the in vitro bacterial DNA repair assay, the in vitro forward gene mutation assay in mouse lymphoma cells, the in vitro chromosomal aberration assay in Chinese hamster lung (CHL) cells, the in vivo micronucleus assay in mice, and the unscheduled DNA synthesis assay in rats. Aripiprazole and a metabolite (2,3-DCPP) were clastogenic in the in vitro chromosomal aberration assay in CHL cells with and without metabolic activation. The metabolite, 2,3-DCPP, increased numerical aberrations in the in vitro assay in CHL cells in the absence of metabolic activation. A positive response was obtained in the in vivo micronucleus assay in mice; however, the response was due to a mechanism not considered relevant to humans.

Impairment of Fertility

Female rats were treated orally with aripiprazole from 2 weeks prior to mating through gestation Day 7 at doses of 2, 6, and 20 mg/kg/day, which are 0.6, 2, and 6 times the MRHD of 30 mg/day based on mg/m^2 body surface area. Estrus cycle irregularities and increased corpora lutea were seen at all doses, but no impairment of fertility was seen. Increased preimplantation loss was seen at 2 and 6 times the MRHD, and decreased fetal weight was seen at 6 times the MRHD.

Male rats were treated orally with aripiprazole from 9 weeks prior to mating through mating at doses of 20, 40, and 60 mg/kg/day, which are 6, 13, and 19 times the MRHD of 30 mg/day based on mg/m^2 body surface area. Disturbances in spermatogenesis were seen at 19 times the MRHD and prostate atrophy was seen at 13 and 19 times the MRHD without impairment of fertility.

13.2 Animal Toxicology and/or Pharmacology

Aripiprazole produced retinal degeneration in albino rats in a 26 week chronic toxicity study at a dose of 60 mg/kg/day and in a 2 year carcinogenicity study at doses of 40 and 60 mg/kg/day which are 13 and 19 times the MRHD of 30 mg/day based on mg/m^2 body surface area. Evaluation of the retinas of albino mice and of monkeys did not reveal evidence of retinal degeneration. Additional studies to further evaluate the mechanism have not been performed. The relevance of this finding to human risk is unknown.

14 CLINICAL STUDIES

14.1 Overview of the Clinical Studies

The efficacy of OPIPZA for the treatment of schizophrenia in patients ages 13 to 17 years, adjunctive treatment of adults with MDD, treatment of irritability associated with autistic disorder in pediatric patients 6 years and older, and treatment of Tourette's disorder in pediatric patients 6 years and older is based on the following adequate and well-controlled studies of another oral aripiprazole product (referred to as "aripiprazole" in this section):

- Four short-term trials and one maintenance trial in adult patients and one short-term trial in pediatric patients ages 13 to 17 years with schizophrenia [see Clinical Studies (14.1)]
- Two short-term trials in adult patients with MDD who had an inadequate response to antidepressant therapy during the current episode [see Clinical Studies (14.3)]
- Two short-term trials in pediatric patients ages 6 to 17 years for the treatment of irritability associated with autistic disorder [see Clinical Studies (14.4)]
- Two short-term trials in pediatric patients ages 6 to 18 years with Tourette's disorder [see Clinical Studies (14.5)]

14.2 Schizophrenia

Adults

The efficacy of aripiprazole in the treatment of schizophrenia was evaluated in five short-term (4 week and 6 week), placebo-controlled trials of acutely relapsed inpatients who predominantly met DSM-III/IV criteria for schizophrenia. Four of the five trials were able to distinguish aripiprazole from placebo, but one study, the smallest, did not. Three of these studies also included an active control group consisting of either risperidone (one trial) or haloperidol (two trials), but they were not designed to allow for a comparison of aripiprazole and the active comparators.

In the four positive trials for aripiprazole, four primary measures were used for assessing psychiatric signs and symptoms. Efficacy was evaluated using the total score on the Positive and Negative Syndrome Scale (PANSS). The PANSS is a 30 item scale that measures positive symptoms of schizophrenia (7 items), negative symptoms of schizophrenia (7 items), and general psychopathology (16 items), each rated on a scale of 1 (absent) to 7 (extreme); total PANSS scores range from 30 to 210. The Clinical Global Impression (CGI) assessment reflects the impression of a skilled observer, fully familiar with the manifestations of schizophrenia, about the overall clinical state of the patient.

In a 4 week trial (n=414) comparing two fixed doses of aripiprazole (15 or 30 mg/day) to placebo, both doses of aripiprazole were superior to placebo in the PANSS total score (Study 1 in Table 26), PANSS positive subscale, and CGI-severity score. In addition, the 15 mg dose was superior to placebo in the PANSS negative subscale.
In a 4 week trial (n=404) comparing two fixed doses of aripiprazole (20 or 30 mg/day) to placebo, both doses of aripiprazole were superior to placebo in the PANSS total score (Study 2 in Table 26), PANSS positive subscale, PANSS negative subscale, and CGI- severity score.
In a 6 week trial (n=420) comparing three fixed doses of aripiprazole (10, 15, or 20 mg/day) to placebo, all three doses of aripiprazole were superior to placebo in the PANSS total score (Study 3 in Table 26), PANSS positive subscale, and the PANSS negative subscale.
In a 6 week trial (n=367) comparing three fixed doses of aripiprazole (2, 5, or 10 mg/day) to placebo, the 10 mg dose of aripiprazole was superior to placebo in the PANSS total score (Study 4 in Table 26), the primary outcome measure of the study. The 2 and 5 mg doses did not demonstrate superiority to placebo on the primary outcome measure.

Thus, the efficacy of 10, 15, 20, and 30 mg daily doses was established in two studies for each dose. Among these doses, there was no evidence that the higher dose groups offered any advantage over the lowest dose group of these studies.

An examination of population subgroups did not reveal any clear evidence of differential responsiveness on the basis of age, gender, or race.

A longer-term trial enrolled 310 inpatients or outpatients meeting DSM-IV criteria for schizophrenia who were, by history, symptomatically stable on other antipsychotic medications for periods of 3 months or longer. These patients were discontinued from their antipsychotic medications and randomized to aripiprazole 15 mg/day or placebo for up to 26 weeks of observation for relapse. Relapse during the double-blind phase was defined as CGI-Improvement score of ≥5 (minimally worse), scores ≥5 (moderately severe) on the hostility or uncooperativeness items of the PANSS, or ≥20% increase in the PANSS total score. Patients receiving aripiprazole 15 mg/day experienced a significantly longer time to relapse over the subsequent 26 weeks compared to those receiving placebo (Study 5 in Figure 6).

Pediatric Patients (13 to 17 years)

The efficacy of aripiprazole in the treatment of schizophrenia in pediatric patients (13 to 17 years of age) was evaluated in one 6-week, placebo-controlled trial of outpatients who met DSM-IV criteria for schizophrenia and had a PANSS score ≥70 at baseline. In this trial (n=302) comparing two fixed doses of aripiprazole (10 or 30 mg/day) to placebo, aripiprazole was titrated starting from 2 mg/day to the target dose in 5 days in the 10 mg/day treatment arm and in 11 days in the 30 mg/day treatment arm. Both doses of aripiprazole were superior to placebo in the PANSS total score (Study 6 in Table 19), the primary outcome measure of the study. The 30 mg/day dosage was not shown to be more efficacious than the 10 mg/day dose. Although maintenance efficacy in pediatric patients has not been systematically evaluated, maintenance efficacy can be extrapolated from adult data along with comparisons of aripiprazole pharmacokinetic parameters in adult and pediatric patients.

Table 19: Schizophrenia Studies (Adults and Pediatric Patients 13 to 17 years)
 |  | Primary Efficacy Measure: PANSS
Study Number | Treatment Group | Mean Baseline Score (SD) | LS Mean Change from Baseline (SE) | Placebo-subtracted Difference [Difference (drug minus placebo) in least-squares mean change from baseline.] (95% CI)
Study 1 | Aripiprazole (15 mg/day) [Doses statistically significantly superior to placebo.] | 98.5 (17.2) | -15.5 (2.40) | -12.6 (-18.9, -6.2)
Study 1 | Aripiprazole (30 mg/day) | 99.0 (19.2) | -11.4 (2.39) | -8.5 (-14.8, -2.1)
Study 1 | Placebo | 100.2 (16.5) | -2.9 (2.36) | --
Study 2 | Aripiprazole (20 mg/day) | 92.6 (19.5) | -14.5 (2.23) | -9.6 (-15.4, -3.8)
Study 2 | Aripiprazole (30 mg/day) | 94.2 (18.5) | -13.9 (2.24) | -9.0 (-14.8, -3.1)
Study 2 | Placebo | 94.3 (18.5) | -5.0 (2.17) | --
Study 3 | Aripiprazole (10 mg/day) | 92.7 (19.5) | -15.0 (2.38) | -12.7 (-19.00, -6.41)
Study 3 | Aripiprazole (15 mg/day) | 93.2 (21.6) | -11.7 (2.38) | -9.4 (-15.71, -3.08)
Study 3 | Aripiprazole (20 mg/day) | 92.5 (20.9) | -14.4 (2.45) | -12.1 (-18.53, -5.68)
Study 3 | Placebo | 92.3 (21.8) | -2.3 (2.35) | --
Study 4 | Aripiprazole (2 mg/day) | 90.7 (14.5) | -8.2 (1.90) | -2.9 (-8.29, 2.47)
Study 4 | Aripiprazole (5 mg/day) | 92.0 (12.6) | -10.6 (1.93) | -5.2 (-10.7, 0.19)
Study 4 | Aripiprazole (10 mg/day) | 90.0 (11.9) | -11.3 (1.88) | -5.9 (-11.3, -0.58)
Study 4 | Placebo | 90.8 (13.3) | -5.3 (1.97) | --
Study 6 Pediatric patients (13 to 17 years) | Aripiprazole (10 mg/day) | 93.6 (15.7) | -26.7 (1.91) | -5.5 (-10.7, -0.21)
Study 6 Pediatric patients (13 to 17 years) | Aripiprazole (30 mg/day) | 94.0 (16.1) | -28.6 (1.92) | -7.4 (-12.7, -2.13)
Study 6 Pediatric patients (13 to 17 years) | Placebo | 94.6 (15.6) | -21.2 (1.93) | --
SD: standard deviation; SE: standard error; LS Mean: least-squares mean; CI: unadjusted confidence interval.

Figure 6: Kaplan-Meier Estimation of Cumulative Proportion of Adults with Relapse (Schizophrenia Study 5)

14.3 Adjunctive Treatment of Adults with Major Depressive Disorder

The efficacy of aripiprazole in the adjunctive treatment of major depressive disorder (MDD) was demonstrated in two short-term (6-week), placebo-controlled trials of adult patients meeting DSM-IV criteria for MDD who had had an inadequate response to prior antidepressant therapy (1 to 3 courses) in the current episode and who had also demonstrated an inadequate response to 8 weeks of prospective antidepressant therapy (paroxetine controlled-release, venlafaxine extended-release, fluoxetine, escitalopram, or sertraline). Inadequate response for prospective treatment was defined as less than 50% improvement on the 17 item version of the Hamilton Depression Rating Scale (HAMD17), minimal HAMD17 score of 14, and a Clinical Global Impressions Improvement rating of no better than minimal improvement. Inadequate response to prior treatment was defined as less than 50% improvement as perceived by the patient after a minimum of 6 weeks of antidepressant therapy at or above the minimal effective dose.

The primary instrument used for assessing depressive symptoms was the Montgomery-Asberg Depression Rating Scale (MADRS), a 10 item clinician-rated scale used to assess the degree of depressive symptomatology. The key secondary instrument was the Sheehan Disability Scale (SDS), a 3 item self-rated instrument used to assess the impact of depression on three domains of functioning with each item scored from 0 (not at all) to 10 (extreme).

In the two trials (n=381, n=362), aripiprazole was superior to placebo in reducing mean MADRS total scores (Studies 1, 2 in Table 28). In one study, aripiprazole was also superior to placebo in reducing the mean SDS score.

In both trials, patients received aripiprazole adjunctive to antidepressants at a dose of 5 mg/day. Based on tolerability and efficacy, doses could be adjusted by 5 mg increments, one week apart. Allowable doses were: 2, 5, 10, 15 mg/day, and for patients who were not on potent CYP2D6 inhibitors fluoxetine and paroxetine, 20 mg/day. The mean final dose at the end point for the two trials was 10.7 and 11.4 mg/day.

An examination of population subgroups did not reveal evidence of differential response based on age, choice of prospective antidepressant, or race. With regard to gender, a smaller mean reduction on the MADRS total score was seen in males than in females.

Table 20: Adjunctive Treatment of Major Depressive Disorder Studies (Adults)
 |  | Primary Efficacy Measure: MADRS
Study Number | Treatment Group | Mean Baseline Score (SD) | LS Mean Change from Baseline (SE) | Placebo-subtracted Difference [Difference (drug minus placebo) in least-squares mean change from baseline.] (95% CI)
Study 1 | Aripiprazole (5 to 20 mg/day) [Doses statistically significantly superior to placebo.] + Antidepressant | 25.2 (6.2) | -8.49 (0.66) | -2.84 (-4.53, -1.15)
Study 1 | -------------------------------
Study 1 | Placebo + Antidepressant | 27.0 (5.5) | -5.65 (0.64) | --
Study 2 | Aripiprazole (5 to 20 mg/day) + Antidepressant | 26.0 (6.0) | -8.78 (0.63) | -3.01 (-4.66, -1.37)
Study 2 | -------------------------------
Study 2 | Placebo + Antidepressant | 26.0 (6.5) | -5.77 (0.67) | --
SD: standard deviation; SE: standard error; LS Mean: least-squares mean; CI: unadjusted confidence interval.

14.4 Irritability Associated with Autistic Disorder

Pediatric Patients (6 to 17 years)

The efficacy of aripiprazole in the treatment of irritability associated with autistic disorder was established in two 8 week, placebo-controlled trials in pediatric patients (6 to 17 years) who met the DSM-IV criteria for autistic disorder and demonstrated behaviors such as tantrums, aggression, self-injurious behavior, or a combination of these problems. Over 75% of these patients were under 13 years of age.

Efficacy was evaluated using two assessment scales: The Aberrant Behavior Checklist (ABC) and the Clinical Global Impression-Improvement (CGI-I) scale. The primary outcome measure in both trials was the change from baseline to endpoint in the Irritability subscale of the ABC (ABC-I). The ABC-I subscale measured symptoms of irritability in autistic disorder.

The results of these trials are as follows:

In one of the 8 week, placebo-controlled trials, pediatric patients 6 to 17 years with autistic disorder (n=98), received daily doses of placebo or aripiprazole 2 to 15 mg/day. Aripiprazole, starting at 2 mg/day with increases allowed up to 15 mg/day based on clinical response, significantly improved scores on the ABC-I subscale and on the CGI-I scale compared with placebo. The mean daily dose of aripiprazole at the end of 8 week treatment was 8.6 mg/day (Study 1 in Table 29).

In the other 8 week, placebo-controlled trial in pediatric patients 6 to 17 years with autistic disorder (n=218), three fixed doses of aripiprazole (5 mg/day, 10 mg/day, or 15 mg/day) were compared to placebo. aripiprazole dosing started at 2 mg/day and was increased to 5 mg/day after one week. After a second week, it was increased to 10 mg/day for patients in the 10 and 15 mg dose arms, and after a third week, it was increased to 15 mg/day in the 15 mg/day treatment arm (Study 2 in Table 21). All three doses of aripiprazole significantly improved scores on the ABC-I subscale compared with placebo.

Table 21: Irritability Associated with Autistic Disorder Studies (Pediatric Patients 6 to 17 years)
 |  | Primary Efficacy Measure: ABC-I
Study Number | Treatment Group | Mean Baseline Score (SD) | LS Mean Change from Baseline (SE) | Placebo-subtracted Difference [Difference (drug minus placebo) in least-squares mean change from baseline.] (95% CI)
Study 1 | Aripiprazole (2 to 15 mg/day) [Doses statistically significantly superior to placebo.] | 29.6 (6.37) | -12.9 (1.44) | -7.9 (-11.7, -4.1)
Study 1 | Placebo | 30.2 (6.52) | -5.0 (1.43) | --
Study 2 | Aripiprazole (5 mg/day) | 28.6 (7.56) | -12.4 (1.36) | -4.0 (-7.7, -0.4)
Study 2 | Aripiprazole (10 mg/day) | 28.2 (7.36) | -13.2 (1.25) | -4.8 (-8.4, -1.3)
Study 2 | Aripiprazole (15 mg/day) | 28.9 (6.41) | -14.4 (1.31) | -6.0 (-9.6, -2.3)
Study 2 | Placebo | 28.0 (6.89) | -8.4 (1.39) | --
SD: standard deviation; SE: standard error; LS Mean: least-squares mean; CI: unadjusted confidence interval.

14.5 Tourette's Disorder

Pediatric Patients (6 to 18 years)

The efficacy of aripiprazole in the treatment of Tourette's disorder was established in one 8 week (7 to 17 years of age) and one 10 week (6 to 18 years of age), placebo-controlled trials in pediatric patients (6 to 18 years of age) who met the DSM-IV criteria for Tourette's disorder and had a Total Tic score (TTS) ≥ 20 to 22 on the Yale Global Tic Severity Scale (YGTSS). The YGTSS is a fully validated scale designed to measure current tic severity. Efficacy was evaluated using two assessment scales: 1) the Total Tic score (TTS) of the YGTSS and 2) the Clinical Global Impressions Scale for Tourette's Syndrome (CGI-TS), a clinician-determined summary measure that takes into account all available patient information. Over 65% of these patients were under 13 years of age.

The primary outcome measure in both trials was the change from baseline to endpoint in the TTS of the YGTSS. Ratings for the TTS are made along 5 different dimensions on a scale of 0 to 5 for motor and vocal tics each. Summation of these 10 scores provides a TTS (i.e., 0 to 50).

The results of these trials are as follows:

In the 8 week, placebo-controlled, fixed-dose trial, pediatric patients 7 to 17 years with Tourette's disorder (n=133), were randomized 1:1:1 to low dose aripiprazole, high dose aripiprazole, or placebo. The target doses for the low and high dose aripiprazole groups were based on weight. Patients < 50 kg in the low dose aripiprazole group started at 2 mg per day with a target dose of 5 mg per day after 2 days. Patients ≥ 50 kg in the low dose aripiprazole group, started at 2 mg per day increased to 5 mg per day after 2 days, with a subsequent increase to a target dose of 10 mg per day at Day 7. Patients <50 kg in the high dose aripiprazole group started at 2 mg per day increased to 5 mg per day after 2 days, with a subsequent increase to a target dose of 10 mg per day at Day 7. Patients ≥ 50 kg in the high dose aripiprazole group, started at 2 mg per day increased to 5 mg per day after 2 days, with a subsequent increase to a dose of 10 mg per day at Day 7 and were allowed weekly increases of 5 mg per day up to a target dose 20 mg per day at Day 21. Aripiprazole (both high and low dose groups) demonstrated statistically significantly improved scores on the YGTSS TTS (Study 1 in Table 22) and on the CGI-TS scale compared with placebo. The estimated improvements on the YGTSS TTS over the course of the study are displayed in Figure 7.

Figure 7: Least Square Means of Change from Baseline in YGTSS TTS by Week in Pediatric Patients 7 to 17 years (Tourette's Disorder Study 1)

In the 10 week, placebo-controlled, flexible-dose trial in pediatric patients 6 to 18 years with Tourette's disorder (n=61), patients received daily doses of placebo or aripiprazole, starting at 2 mg/day with increases allowed up to 20 mg/day based on clinical response. Aripiprazole demonstrated statistically significantly improved scores on the YGTSS TTS scale compared with placebo (Study 2 in Table 22). The mean daily dose of aripiprazole at the end of 10-week treatment was 6.54 mg/day.

Table 22: Tourette's Disorder Studies (Pediatric Patients)
 |  | Primary Efficacy Measure: YGTSS TTS
Study Number Population (Age Range) | Treatment Group | Mean Baseline Score (SD) | LS Mean Change from Baseline (SE) | Placebo-subtracted Difference [Difference (drug minus placebo) in least-squares mean change from baseline.] (95% CI)
Study 1 Pediatric patients (7 to 17 years) | Aripiprazole (low dose) [Doses statistically significantly superior to placebo.] | 29.2 (5.63) | -13.4 (1.59) | -6.3 (-10.2, -2.3)
Study 1 Pediatric patients (7 to 17 years) | Aripiprazole (high dose) | 31.2 (6.40) | -16.9 (1.61) | -9.9 (-13.8, -5.9)
Study 1 Pediatric patients (7 to 17 years) | Placebo | 30.7 (5.95) | -7.1 (1.55) | --
Study 2 Pediatric patients (6 to 18 years) | Aripiprazole (2 to 20 mg/day) | 28.3 (5.51) | -15.0 (1.51) | -5.3 (-9.8, -0.9)
Study 2 Pediatric patients (6 to 18 years) | Placebo | 29.5 (5.60) | -9.6 (1.64) | --
SD: standard deviation; SE: standard error; LS Mean: least-squares mean; CI: unadjusted confidence interval.

16 HOW SUPPLIED/STORAGE AND HANDLING

How Supplied

OPIPZA is available in the strengths and packages listed in Table 23.

Table 23: OPIPZA Presentations
Strength | Color/Shape | Markings | Pack Size | NDC Code
2 mg | 1 cm × 1.2 cm Rectangular white film | A2 | 30 Pouches of 1 | 15370-401-30
5 mg | 2 cm × 1.5 cm Rectangular white film | A5 | 30 Pouches of 1 | 15370-402-30
10 mg | 2 cm × 3 cm Rectangular white film | A10 | 30 Pouches of 1 | 15370-403-30

Storage

Store at 20°C to 25°C (68°F to 77°F); excursions permitted between 15°C to 30°C (59°F to 86°F) [see USP Controlled Room Temperature].

17 PATIENT COUNSELING INFORMATION

Advise the patient to read the FDA-approved patient labeling (Medication Guide and Instructions for Use).

Suicidal Thoughts and Behaviors

Advise patients and caregivers to look for the emergence of suicidal ideation and behavior, especially early during treatment and when the dose is adjusted up or down, and instruct them to report such symptoms to the healthcare provider [see Boxed Warning, and Warnings and Precautions (5.1)].

Neuroleptic Malignant Syndrome

Counsel patients about a potentially fatal adverse reaction, Neuroleptic Malignant Syndrome (NMS) that has been reported in association with administration of antipsychotic drugs. Advise patients, family members, or caregivers to contact a health care provider or report to the emergency room if they experience signs and symptoms of NMS [see Warnings and Precautions (5.4)].

Tardive Dyskinesia

Counsel patients on the signs and symptoms of tardive dyskinesia and to contact their health care provider if these abnormal movements occur [see Warnings and Precautions (5.5)].

Metabolic Changes

Educate patients about the risk of metabolic changes, how to recognize symptoms of hyperglycemia and diabetes mellitus, and the need for specific monitoring, including blood glucose, lipids, and weight [see Warnings and Precautions (5.6)].

Pathological Gambling and Other Compulsive Behaviors

Advise patients and their caregivers of the possibility that they may experience compulsive urges to shop, intense urges to gamble, compulsive sexual urges, binge eating and/or other compulsive urges and the inability to control these urges while taking OPIPZA . In some cases, but not all, the urges were reported to have stopped when the dose was reduced or stopped [see Warnings and Precautions (5.7)].

Orthostatic Hypotension and Syncope

Educate patients about the risk of orthostatic hypotension and syncope, especially early in treatment, and also at times of re-initiating treatment or increases in dosage [see Warnings and Precautions (5.8)].

Leukopenia/Neutropenia

Advise patients with a pre-existing low WBC count or a history of drug-induced leukopenia/neutropenia that they should have their CBC monitored while receiving OPIPZA [see Warnings and Precautions (5.10)].

Potential for Cognitive and Motor Impairment

Inform patients that OPIPZA has the potential to impair judgment, thinking, or motor skills. Caution patients about performing activities requiring mental alertness, such as operating hazardous machinery or operating a motor vehicle until they are reasonably certain that OPIPZA therapy does not affect them adversely [see Warnings and Precautions (5.12)].

Concomitant Medication

Advise patients to inform their healthcare providers of any changes to their current prescription or over-the-counter medications because there is a potential for clinically significant interactions [see Drug Interactions (7.1)].

Heat Exposure and Dehydration

Educate patients regarding appropriate care in avoiding overheating and dehydration [see Warnings and Precautions (5.13)].

Pregnancy

Advise patients that OPIPZA may cause extrapyramidal and/or withdrawal symptoms (agitation, hypertonia, hypotonia, tremor, somnolence, respiratory distress, and feeding disorder) in a neonate. Advise patients to notify their healthcare provider if they become pregnant or intend to become pregnant during treatment with OPIPZA. Advise patients that there is a pregnancy registry that monitors pregnancy outcomes in women exposed to OPIPZA during pregnancy [see Use in Specific Populations (8.1)].

Administration Information

Advise the patient of the following [see Dosage and Administration (2.5)]:

- Administer OPIPZA with or without food.
- Apply OPIPZA on top of the tongue where it dissolves in saliva and can be swallowed in a normal manner without the need for water or other liquids.
- Refrain from chewing the film or swallowing an undissolved film. Do not cut or split OPIPZA.
- Administer only one oral film at a time. If an additional film is needed to complete the dosage, administer after the previous film has completely dissolved.

Distributed by
Carwin Pharmaceutical Associates, LLC
Hazlet, NJ 07730

Manufactured by
Xiamen LP Pharmaceutical Co., Ltd.
2010 Wengjiao West Road, Xiamen, Fujian 361027, China

MEDICATION GUIDE
OPIPZA™ (o-PIP-sah)
(aripiprazole) oral film

What is the most important information I should know about OPIPZA?

OPIPZA may cause serious side effects, including:

- Increased risk of death in elderly people with dementia-related psychosis: Medicines like OPIPZA can increase the risk of death in elderly people who have lost touch with reality (psychosis) due to confusion and memory loss (dementia). OPIPZA is not for the treatment of people with dementia-related psychosis.
- Increased risk of suicidal thoughts and actions: OPIPZA and antidepressant medicines increase the risk of suicidal thoughts and actions in people 24 years of age and younger, especially within the first few months of treatment or when the dose is changed.
  - Depression and other mental illnesses are the most important causes of suicidal thoughts and actions.
  How can I watch for and try to prevent suicidal thoughts and actions in myself or a family member?
  - Pay close attention to any changes, especially sudden changes, in mood, behaviors, thoughts, or feelings or if you develop suicidal thoughts or actions. This is very important when OPIPZA or the antidepressant medicine is started or when the dose is changed.
  - Call your healthcare provider right away to report new or sudden changes in mood, behavior, thoughts, or feelings of if you develop suicidal thoughts or actions.
  - Keep all follow-up visits with your healthcare provider as scheduled. Call your healthcare provider between visits as needed, especially if you have concerns about symptoms.
  Call a healthcare provider right away if you or your family member has any of the following symptoms, especially if they are new, worse, or worry you:

- thoughts about suicide or dying
- attempts to commit suicide
- new or worsening depression
- new or worsening anxiety
- feeling very agitated or restless
- panic attacks

- trouble sleeping (insomnia)
- new or worsening irritability
- acting aggressive, being angry, or violent
- acting on dangerous impulses
- an extreme increase in activity and talking (mania)
- other unusual changes in behavior or mood

See "What are the possible side effects of OPIPZA?" for more information about side effects.

What is OPIPZA?

OPIPZA is a prescription medicine used to treat:

- schizophrenia in people ages 13 years and older
- major depressive disorder (MDD) in adults when OPIPZA is used along with antidepressant medicines
- irritability associated with autistic disorder in children ages 6 years and older
- Tourette's disorder in children ages 6 years and older

It is not known if OPIPZA is safe and effective for treatment in children:

- under 13 years of age with schizophrenia
- with MDD
- under 6 years of age with irritability associated with autistic disorder
- under 6 years of age with Tourette's disorder

Who should not take OPIPZA?

Do not take OPIPZA if you are allergic to aripiprazole or any of the ingredients in OPIPZA. See the end of this Medication Guide for a complete list of ingredients in OPIPZA.

Before taking OPIPZA, tell your healthcare provider about all your medical conditions, including if you:

- have or had diabetes or high blood sugar in you or your family. Your healthcare provider should check your blood sugar before you start OPIPZA and during your treatment with OPIPZA.
- have or had high levels of total cholesterol, LDL cholesterol, or triglycerides, or low levels of HDL cholesterol
- have or had low or high blood pressure
- have or had heart problems or stroke
- have or had low white blood cell counts
- have or had seizures (convulsions)
- are pregnant or plan to become pregnant. OPIPZA may harm your unborn baby. Taking OPIPZA during your third trimester of pregnancy may cause your baby to have abnormal muscle movements or withdrawal symptoms after birth. Talk to your healthcare provider about the risk to your unborn baby if you take OPIPZA during pregnancy.
  - Tell your healthcare provider right away if you become pregnant during treatment with OPIPZA.
  - If you become pregnant during treatment with OPIPZA, talk to your healthcare provider about registering with the National Pregnancy Registry for Atypical Antipsychotics. You can register by calling 1-866-961-2388 or go to http://womensmentalhealth.org/clinical-and-research-programs/pregnancyregistry/
- are breastfeeding or plan to breastfeed. OPIPZA passes into your breast milk. Talk to your healthcare provider about the best way to feed your baby during treatment with OPIPZA.

Tell your healthcare provider about all the medicines that you take, including prescription and over-the-counter medicines, vitamins, and herbal supplements.

OPIPZA and other medicines may affect each other causing possible serious side effects. OPIPZA may affect the way other medicines work, and other medicines may affect how OPIPZA works.

Your healthcare provider can tell you if it is safe to take OPIPZA with your other medicines. Do not start or stop any medicines during treatment with OPIPZA without first talking to your healthcare provider.

Know the medicines you take. Keep a list of your medicines to show your healthcare provider and pharmacist when you get a new medicine.

How should I take OPIPZA?

- Take OPIPZA exactly as your healthcare provider tells you to take it. Do not change the dose or stop taking OPIPZA unless your healthcare provider tells you to.
- Take OPIPZA with or without food.
- Each OPIPZA film comes in a sealed child-resistant pouch. Do not open the pouch until you are ready to take your dose of OPIPZA.
- Let the film dissolve on your tongue before swallowing it.
- Do not chew the film or swallow it whole.
- Do not cut or split the film.
- See the detailed Instructions for Use for information on how to take a dose of OPIPZA.
- If you take too much OPIPZA, call your healthcare provider or Poison Help line at 1-800-222-1222, or go to the nearest hospital emergency room right away.

What should I avoid while taking OPIPZA?

- Do not drive, operate heavy machinery, or do other dangerous activities until you know how OPIPZA affects you. OPIPZA may make you drowsy or may affect your judgement, thinking, or motor skills.
- Do not become too hot or dehydrated during treatment with OPIPZA.
  - Do not exercise too much.
  - In hot weather, stay inside in a cool place if possible.
  - Stay out of the sun.
  - Do not wear too much clothing or heavy clothing.
  - Drink plenty of water.

What are the possible side effects of OPIPZA?

OPIPZA may cause serious side effects, including:

- See "What is the most important information I should know about OPIPZA?"
- Stroke (cerebrovascular problems) in elderly people with dementia-related psychosis that can lead to death
- Neuroleptic malignant syndrome (NMS), a serious condition that can lead to death. Call your healthcare provider right away or go to the nearest emergency room if you have some or all of the following signs and symptoms of NMS:

- high fever
- confusion
- changes in pulse, heart rate, and blood pressure

- stiff muscles
- sweating

- Uncontrolled body movements (tardive dyskinesia). OPIPZA may cause movements that you cannot control in your face, tongue, or other body parts. Tardive dyskinesia may not go away, even if you stop taking OPIPZA. Tardive dyskinesia may also start after you stop taking OPIPZA.
- Problems with your metabolism such as:
  - High blood sugar (hyperglycemia) and diabetes. Increases in blood sugar can happen in some people who are treated with OPIPZA. Extremely high blood sugar can lead to coma or death. If you have diabetes or risk factors for diabetes such as being overweight, or a family history of diabetes, your healthcare provider should check your blood sugar before you start treatment and during your treatment with OPIPZA.
    Call your healthcare provider if you have any of these symptoms of high blood sugar while receiving OPIPZA:

- feel very thirsty
- feel very hungry
- feel sick to your stomach

- need to urinate more than usual
- feel weak or tired
- feel confused, or your breath smells fruity

- Increased fat levels (cholesterol and triglycerides) in your blood. You healthcare provider may check your cholesterol and triglyceride levels during treatment with OPIPZA.
- Weight gain. You and your healthcare provider should check your weight regularly during treatment with OPIPZA.

- Unusual and uncontrollable (compulsive) urges. Some people taking OPIPZA have had unusual strong urges to gamble and gambling that cannot be controlled (compulsive gambling). Other compulsive urges can happen including sexual urges, shopping, and binge eating or eating that you cannot control. If you or your family members notice that you are having unusual urges or behaviors, talk to your healthcare provider.
- Decreased blood pressure (orthostatic hypotension) and fainting. You may feel lightheaded or faint when you rise too quickly from a sitting or lying position.
- Falls. OPIPZA may make you sleepy or dizzy, may cause a decrease in your blood pressure when changing position (orthostatic hypotension), and can slow your thinking and motor skills which may lead to falls that can cause fractures or other injuries.
- Low white blood cell count. Your healthcare provider may do blood cell count tests during your first few months of treatment with OPIPZA.
- Seizures (convulsions).
- Sleepiness, drowsiness, feeling tired, difficulty thinking and doing normal activities. See "What should I avoid while taking OPIPZA?"
- Problems controlling your body temperature so that you feel too warm. See "What should I avoid while taking OPIPZA?"
- Difficulty swallowing that can cause food or liquid to get into your lungs.

The most common side effects of OPIPZA in adults include:

- feeling like you need to move (akathisia)
- trouble sleeping (insomnia)
- restlessness

- constipation
- feeling tired
- blurred vision

The most common side effects of OPIPZA in children include:

- feeling sleepy or tired
- headache
- vomiting
- nausea
- increased or decreased appetite

- increased saliva or drooling
- uncontrolled movements, muscle stiffness, or tremors
- fever
- cold symptoms
- having no energy

These are not all of the possible side effects of OPIPZA.

Call your doctor for medical advice about side effects. You may report side effects to FDA at 1-800-FDA-1088.

How should I store OPIPZA?

- Store OPIPZA at room temperature between 68°F to 77°F (20°C to 25°C).

Keep OPIPZA and all medicines out of the reach of children.

General information about the safe and effective use of OPIPZA

Medicines are sometimes prescribed for purposes other than those listed in a Medication Guide. Do not use OPIPZA for a condition for which it was not prescribed. Do not give OPIPZA to other people, even if they have the same symptoms you have. It may harm them. You can ask your pharmacist or healthcare provider for information about OPIPZA that is written for health professionals.

What are the ingredients in OPIPZA?

Active ingredient: aripiprazole.

Inactive ingredients: hydroxypropyl cellulose, sodium lauryl sulfate, and sucralose. Imprinting ink contains glycerin, FD&C Blue No.1, polysorbate 20, and propylene glycol.

Distributed by
Carwin Pharmaceutical Associates, LLC
Hazlet, NJ 07730

Manufactured by
Xiamen LP Pharmaceutical Co., Ltd.
2010 Wengjiao West Road, Xiamen, Fujian 361027, China

For more information about OPIPZA go to https://carwinpharma.com/opipza/ or call 1-877-676-0778.

This Medication Guide has been approved by the U.S. Food and Drug Administration.

Issued: 8/2024

INSTRUCTIONS FOR USE OPIPZA™ (o-PIP-sah) (aripiprazole) oral film

This Instructions for Use contains information on how to take OPIPZA.

Figure A

Important Information You Need to Know Before Taking OPIPZA.

- Do not take OPIPZA until:
  - you have read and understand these instructions.
  - you have reviewed the steps with your healthcare provider on how to take it.
  - you know the right time, how often, and the dose to take.
  - you feel comfortable with how to use OPIPZA.
  - If you are not sure about how or when to take OPIPZA, call your healthcare provider.
- OPIPZA is for oral use only (taken by mouth).
- Take OPIPZA with or without food.
- Each OPIPZA film comes in a sealed child-resistant pouch. Do not open the pouch until you are ready to take your dose of OPIPZA.
- Do not chew the film or swallow it whole.
- Do not cut or split the film.
- Check the expiration date printed on the pouch. Do not take OPIPZA if it is expired or if the pouch has been previously cut or pierced. Instead, throw away OPIPZA in your household trash and get a new pouch that is not expired or damaged.

Step 1. Preparing to Take OPIPZA

- Wash and dry your hands before handling and taking OPIPZA (see Figure B).
  Figure B
- Remove the number of pouches that you need for your prescribed dose from the OPIPZA carton.
- If you need to take more than 1 OPIPZA film for your dose, open only 1 pouch and take only 1 film at a time.

Step 2. Opening the OPIPZA Pouch

- Fold the pouch along the dashed line.
- Find the slit, the arrow, and the words "TO OPEN" on the OPIPZA pouch. Carefully tear the pouch in the direction of the arrow starting at the slit to open the pouch (see Figure C).

Figure C

Step 3. Taking OPIPZA

- Carefully remove the film from the OPIPZA pouch (see Figure D).
  If the film tears or dissolves in your hands (hands were not dry enough) when it is removed from the pouch, throw away (dispose of) the film as described below (see "Disposing of OPIPZA") and get a new film. Repeat steps 1 to 3 with the new film.

Figure D

- Take the OPIPZA film right away after opening the pouch and removing the film.
- Do not split or cut the OPIPZA film.
- Place the entire OPIPZA film on the top of your tongue and close your mouth. Let the film dissolve on your tongue before swallowing it. The film will dissolve quickly (see Figure E).
- Do not chew the film or swallow the film whole.
- Do not rinse your mouth with liquid.

Figure E

If you need more than 1 film for your prescribed dose wait until the previous film has completely dissolved before taking another OPIPZA film. Repeat steps 1 to 3 with each additional film that you need to take for your prescribed dose.

When you are finished taking OPIPZA, wash and dry your hands.

Disposing of OPIPZA

- Throw away (dispose of) any unused or expired OPIPZA in your household trash.
- Throw away the empty pouches in your household trash.

Storing OPIPZA

- Store OPIPZA at room temperature between 68°F to 77°F (20°C to 25°C).
- Keep OPIPZA in the unopened pouch until you are ready to take your dose.
- Keep OPIPZA and all medicines out of the reach of children.

Distributed by
Carwin Pharmaceutical Associates, LLC
Hazlet, NJ 07730

Manufactured by
Xiamen LP Pharmaceutical Co., Ltd.
2010 Wengjiao West Road, Xiamen, Fujian 361027, China

For more information or support regarding OPIPZA: Call 1-877-676-0778

The Instructions for Use has been approved by the U.S. Food and Drug Administration. Approved: 8/2024

PRINCIPAL DISPLAY PANEL - 2 mg Film Pouch Carton

NDC 15370-401-30

OPIPZA™
(aripiprazole) oral film

2 mg

Do not cut or chew the oral film

Pharmacist: Dispense the enclosed
Medication Guide to each patient.

30 pouches each containing 1 oral film
Rx Only

PRINCIPAL DISPLAY PANEL - 5 mg Film Pouch Carton

NDC 15370-402-30

OPIPZA™
(aripiprazole) oral film

5 mg

Do not cut or chew the oral film

Pharmacist: Dispense the enclosed
Medication Guide to each patient.

30 pouches each containing 1 oral film
Rx Only

PRINCIPAL DISPLAY PANEL - 10 mg Film Pouch Carton

NDC 15370-403-30

OPIPZA™
(aripiprazole) oral film

10 mg

Do not cut or chew the oral film

Pharmacist: Dispense the enclosed
Medication Guide to each patient.

30 pouches each containing 1 oral film
Rx Only